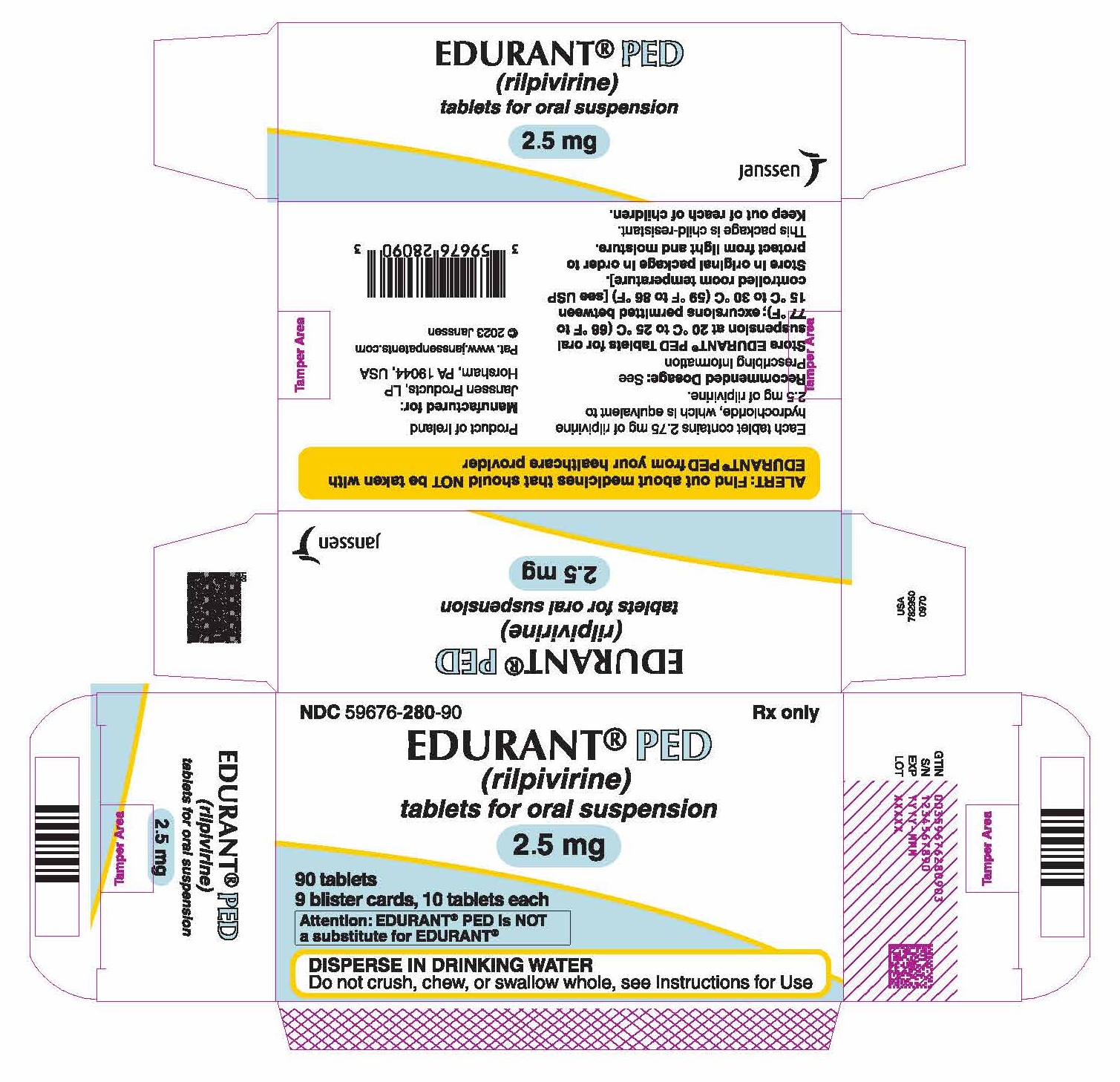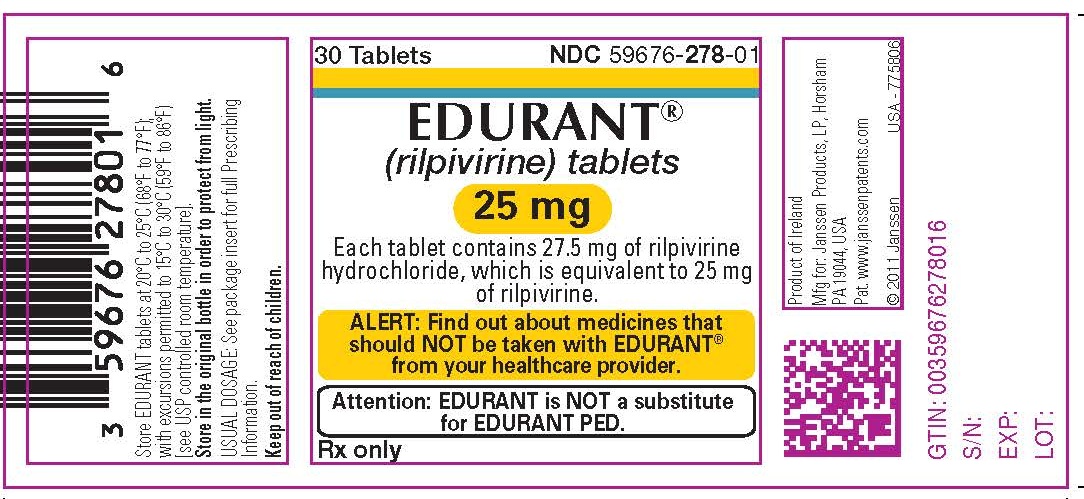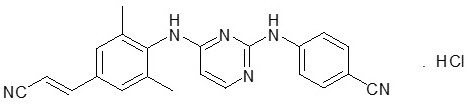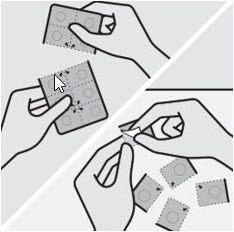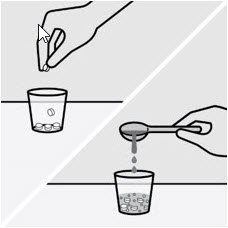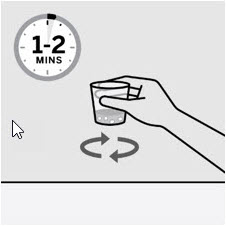 DRUG LABEL: EDURANT
NDC: 59676-278 | Form: TABLET, FILM COATED
Manufacturer: Janssen Products, LP
Category: prescription | Type: HUMAN PRESCRIPTION DRUG LABEL
Date: 20250828

ACTIVE INGREDIENTS: RILPIVIRINE HYDROCHLORIDE 25 mg/1 1
INACTIVE INGREDIENTS: CROSCARMELLOSE SODIUM; MAGNESIUM STEARATE; LACTOSE MONOHYDRATE; POVIDONE K30; POLYSORBATE 20; SILICON DIOXIDE; MICROCRYSTALLINE CELLULOSE; HYPROMELLOSE 2910 (6 MPA.S); POLYETHYLENE GLYCOL 3000; TITANIUM DIOXIDE; TRIACETIN

HIGHLIGHTS OF PRESCRIBING INFORMATION

These highlights do not include all the information needed to use EDURANT safely and effectively. See full prescribing information for EDURANT.
EDURANT®(rilpivirine) tablets, for oral use
EDURANT®PED (rilpivirine) tablets, for oral suspension
Initial U.S. Approval: 2011

RECENT MAJOR CHANGES

Indications and Usage (1.1) | 03/2024
Dosage and Administration (2.1, 2.3, 2.4, 2.5) | 03/2024
Warnings and Precautions (5.6) | 03/2024

1 INDICATIONS AND USAGE

EDURANT and EDURANT PED are a human immunodeficiency virus type 1 (HIV-1) specific, non-nucleoside reverse transcriptase inhibitor (NNRTI) indicated in combination with other antiretroviral agents for the treatment of HIV-1 infection in treatment-naïve patients 2 years of age and older and weighing at least 14 kg with HIV-1 RNA less than or equal to 100,000 copies/mL. (1.1).

Limitations of Use:

- More EDURANT treated subjects with HIV-1 RNA greater than 100,000 copies/mL at the start of therapy experienced virologic failure (HIV-1 RNA ≥50 copies/mL) compared to EDURANT treated subjects with HIV-1 RNA less than or equal to 100,000 copies/mL. (1.1, 14)

EDURANT is indicated in combination with VOCABRIA (cabotegravir), for short-term treatment of HIV-1 infection in adults and adolescents 12 years and older and weighing at least 35 kg who are virologically suppressed (HIV-1 RNA less than 50 copies/mL) on a stable regimen with no history of treatment failure and with no known or suspected resistance to either cabotegravir or rilpivirine. (1.2)

2 DOSAGE AND ADMINISTRATION

- One 25 mg EDURANT tablet taken once daily with a meal for patients weighing at least 25 kg. (2.2)
- Pediatric patients 2 years of age and older and weighing at least 14 kg to less than 25 kg: Dosage of EDURANT PED is based on body weight. (2.3)
- EDURANT PED must be dispersed in drinking water and taken with a meal. (2.4)
- Do not substitute EDURANT tablets and EDURANT PED tablets for oral suspension on a milligram-per-milligram basis due to differing pharmacokinetic profiles. (2.1, 5.6)
- See full prescribing information for dosing information when used in combination with cabotegravir. (2.6)
- For pregnant patients who are already on a stable EDURANT regimen prior to pregnancy and who are virologically suppressed (HIV-1 RNA less than 50 copies per mL) the recommended dosage in adults and pediatric patients weighing more than 25 kg is one 25 mg tablet once daily taken orally with a meal. (2.5, 12.3)
- Rifabutin coadministration: Take two 25 mg tablets of EDURANT once daily with a meal for the duration of the rifabutin coadministration. (2.7)

3 DOSAGE FORMS AND STRENGTHS

- EDURANT: 25 mg tablets (3)
- EDURANT PED: 2.5 mg tablets for oral suspension (3)

4 CONTRAINDICATIONS

Coadministration of EDURANT or EDURANT PED is contraindicated with drugs where significant decreases in rilpivirine plasma concentrations may occur, which may result in loss of virologic response and possible resistance and cross-resistance. (4)

5 WARNINGS AND PRECAUTIONS

- Skin and Hypersensitivity Reactions: Severe skin and hypersensitivity reactions have been reported during postmarketing experience, including cases of Drug Reaction with Eosinophilia and Systemic Symptoms (DRESS), with rilpivirine-containing regimens. Immediately discontinue treatment if hypersensitivity or rash with systemic symptoms or elevations in hepatic serum biochemistries develop and closely monitor clinical status, including hepatic serum biochemistries. (5.1)
- Hepatotoxicity: Hepatic adverse events have been reported in patients with underlying liver disease, including hepatitis B or C virus co-infection, or in patients with elevated baseline transaminases. A few cases of hepatotoxicity have occurred in patients with no pre-existing hepatic disease. Monitor liver function tests before and during treatment with EDURANT or EDURANT PED in patients with underlying hepatic disease, such as hepatitis B or C virus co-infection, or marked elevations in transaminase. Also consider monitoring liver functions tests in patients without pre-existing hepatic dysfunction or other risk factors. (5.2)
- Depressive Disorders: Severe depressive disorders have been reported. Immediate medical evaluation is recommended for severe depressive disorders. (5.3)
- Patients may develop immune reconstitution syndrome. (5.5)

6 ADVERSE REACTIONS

The most common adverse reactions to EDURANT or EDURANT PED (incidence >2%) of at least moderate to severe intensity (≥ Grade 2) were depressive disorders, headache, insomnia and rash. (6.1)

To report SUSPECTED ADVERSE REACTIONS, contact Janssen Products, LP at 1-800-526-7736 or FDA at 1-800-FDA-1088 or www.fda.gov/medwatch.

7 DRUG INTERACTIONS

- Consider alternatives to EDURANT or EDURANT PED when coadministered with drugs with a known risk of torsade de pointes. (5.4)
- EDURANT and EDURANT PED should not be used in combination with NNRTIs. (4, 7)
- Coadministration of EDURANT or EDURANT PED with drugs that induce or inhibit CYP3A may affect the plasma concentrations of rilpivirine. (4, 7)
- Coadministration of EDURANT or EDURANT PED with drugs that increase gastric pH may decrease plasma concentrations of rilpivirine. (4, 7)
- Refer to the Full Prescribing Information for other drugs that should not be coadministered with EDURANT or EDURANT PED and for other drugs that may require a change in dose or regimen. (7)

8 USE IN SPECIFIC POPULATIONS

- Pregnancy: Total rilpivirine exposures were generally lower during pregnancy compared to the postpartum period. (2.5, 8.1, 12.3)

FULL PRESCRIBING INFORMATION

1 INDICATIONS AND USAGE

1.1 Treatment of HIV-1 in Treatment-Naïve Patients

EDURANT and EDURANT PED, in combination with other antiretroviral agents, is indicated for the treatment of human immunodeficiency virus type 1 (HIV-1) infection in antiretroviral treatment-naïve patients 2 years of age and older and weighing at least 14 kg with plasma HIV-1 RNA less than or equal to 100,000 copies/mL at the start of therapy.

Limitations of Use

- More EDURANT treated subjects with HIV-1 RNA greater than 100,000 copies/mL at the start of therapy experienced virologic failure (HIV-1 RNA ≥50 copies/mL) compared to EDURANT treated subjects with HIV-1 RNA less than or equal to 100,000 copies/mL [see Clinical Studies (14.1)] .

1.2 Treatment of HIV-1 in Combination with Cabotegravir

EDURANT is indicated in combination with VOCABRIA (cabotegravir) for short-term treatment of HIV-1 infection in adults and adolescents 12 years and older and weighing at least 35 kg who are virologically suppressed (HIV-1 RNA less than 50 copies/mL) on a stable antiretroviral regimen with no history of treatment failure and with no known or suspected resistance to either cabotegravir or rilpivirine, for use as [see Dosage and Administration (2.6)] :

- oral lead-in to assess the tolerability of rilpivirine prior to administration of rilpivirine extended-release injectable suspension, a component of CABENUVA (cabotegravir extended-release injectable suspension; rilpivirine extended-release injectable suspension).
- oral therapy for patients who will miss planned injection dosing with CABENUVA (cabotegravir extended-release injectable suspension; rilpivirine extended-release injectable suspension).

2 DOSAGE AND ADMINISTRATION

2.1 Overview of Different Dosage Forms

EDURANT is available in two dosage forms:

- EDURANT 25 mg film-coated tablets for adults and pediatric patients weighing at least 25 kg.
- EDURANT PED 2.5 mg tablets for oral suspension should only be given to pediatric patients weighing at least 14 kg to less than 25 kg [see Dosage and Administration (2.3)] .

Do not substitute EDURANT tablets and EDURANT PED tablets for oral suspension on a milligram-per-milligram basis due to differing pharmacokinetic profiles. A difference in bioavailability between 1 × 25 mg film-coated tablet and 10 × 2.5 mg tablets for oral suspension was observed; therefore, they are NOT substitutable [see Warnings and Precautions (5.6)and Clinical Pharmacology (12.3)].

Take EDURANT and EDURANT PED once daily with a meal in combination with other antiretrovirals [see Clinical Pharmacology (12.3)].

2.2 Recommended Dosage in Treatment-Naïve Adult Patients

The recommended dosage of EDURANT in adult patients is one 25 mg tablet taken orally once daily with a meal [see Use in Specific Populations (8.1)and Clinical Pharmacology (12.3)] .

2.3 Recommended Dosage in Treatment-Naïve Pediatric Patients 2 Years of Age and Older and Weighing at least 14 kg

The recommended dosage of EDURANT and EDURANT PED in pediatric patients 2 years of age and older and weighing at least 14 kg is based on body weight (see Table 1). Both EDURANT and EDURANT PED should be taken orally once daily with a meal [see Use in Specific Populations (8.4)and Clinical Pharmacology (12.3)] .

Table 1: Recommended Dosage of EDURANT and EDURANT PED for Pediatric Patients
Body Weight (kg) | EDURANT 25 mg Tablets | EDURANT PED 2.5 mg Tablets for Oral Suspension | Total Daily Dose
14 kg to less than 20 kg | Not recommended | 5 tablets once daily | 12.5 mg EDURANT PED once daily
20 kg to less than 25 kg | Not recommended | 6 tablets once daily | 15 mg EDURANT PED once daily
Greater than or equal to 25 kg | 1 tablet once daily | Not recommended | 25 mg EDURANT once daily

2.4 Preparation and Administration Instructions for EDURANT PED Only

Advise patients or caregivers of patients taking EDURANT PED to refer to the Instructions for Use to properly prepare and take the medication.

EDURANT PED must be dispersed in drinking water and taken immediately with a meal. If not taken immediately, then the oral suspension should be discarded, and a new dose of medicine should be prepared. The patient should not chew or swallow EDURANT PED whole. The following instructions should be followed:

- Place the tablets for oral suspension in a cup, add 5 mL (1 teaspoon) of drinking water at room temperature. Do not crush the tablets.
- Swirl the cup carefully for 1–2 minutes to disperse the tablets. The oral suspension will start to look cloudy.
- Take all the prepared oral suspension immediately or to aid in administration, the oral suspension can be further diluted with 5 mL (1 teaspoon) of drinking water, milk, orange juice or applesauce. Swirl and take all the medicine immediately. A spoon can be used if needed.
- Make sure the entire dose is taken and no medicine is left in the cup. If required, add another 5 mL (1 teaspoon) of drinking water (or alternative beverage or soft food), swirl and drink immediately.

2.5 Recommended Dosage During Pregnancy

For pregnant patients who are already on a stable EDURANT regimen prior to pregnancy and who are virologically suppressed (HIV-1 RNA less than 50 copies per mL) the recommended dosage in adults and pediatric patients weighing at least 25 kg is one 25 mg tablet once daily taken orally with a meal. Refer to Table 1 for dosing recommendations for pediatric patients [see Dosage and Administration (2.2, 2.3)]. Lower exposures of rilpivirine were observed during pregnancy, therefore viral load should be monitored closely [see Use in Specific Populations (8.1)and Clinical Pharmacology (12.3)] .

2.6 Recommended Dosage in Combination with Cabotegravir in Adults and Adolescents 12 Years of Age and Older and Weighing at least 35 kg

Consult the prescribing information for CABENUVA (cabotegravir extended-release injectable suspension; rilpivirine extended-release injectable suspension) before initiating EDURANT to ensure therapy with CABENUVA is appropriate.

Oral Lead-In Dosing to Assess Tolerability of Rilpivirine

Oral lead-in should be used for approximately 1 month (at least 28 days) to assess the tolerability of rilpivirine prior to the initiation of CABENUVA. The recommended oral daily dose is one 25 mg tablet of EDURANT (rilpivirine) in combination with one 30 mg tablet of VOCABRIA (cabotegravir). Take EDURANT with VOCABRIA (cabotegravir) orally once daily at approximately the same time each day with a meal [see Clinical Pharmacology (12.3)].

Because EDURANT is indicated in combination with VOCABRIA (cabotegravir), the prescribing information for VOCABRIA (cabotegravir) tablets should also be consulted.

The last oral dose should be taken on the same day injections with CABENUVA are started.

Oral Dosing to Replace Planned Missed Injections of CABENUVA

Planned Missed Injections for Patients on Monthly Dosing Schedule

If a patient plans to miss a scheduled monthly injection of CABENUVA by more than 7 days, take daily oral therapy for up to 2 months to replace missed injection visits. The recommended oral daily dose is one 25 mg tablet of EDURANT and one 30 mg tablet of VOCABRIA (cabotegravir). Take EDURANT with VOCABRIA (cabotegravir) at approximately the same time each day with a meal. The first dose of oral therapy should be initiated at approximately the same time as the planned missed injection and continued until the day injection dosing is restarted. For oral therapy with EDURANT and VOCABRIA of durations greater than 2 months, an alternative oral regimen is recommended, which may include EDURANT. See full prescribing information for CABENUVA to resume monthly injection dosing.

Planned Missed Injections for Patients on Every-2-Month Dosing Schedule

If a patient plans to miss a scheduled every-2-month injection of CABENUVA by more than 7 days, take daily oral therapy for a duration of up to 2 months to replace 1 missed scheduled every-2-month injection. The recommended oral daily dose is one 25 mg tablet of EDURANT and one 30 mg tablet of VOCABRIA (cabotegravir). Take EDURANT with VOCABRIA (cabotegravir) at approximately the same time each day with a meal. The first dose of oral therapy should be initiated at approximately the same time as the planned missed injection and continued until the day injection dosing is restarted. For oral therapy with EDURANT and VOCABRIA of durations greater than 2 months, an alternative oral regimen is recommended, which may include EDURANT. See full prescribing information for CABENUVA to resume every-2-month injection dosing.

2.7 Recommended Dosage with Rifabutin Coadministration

If EDURANT is coadministered with rifabutin, the EDURANT dose should be increased to 50 mg (two 25 mg tablets) once daily, taken with a meal. When rifabutin coadministration is stopped, the EDURANT dose should be decreased to 25 mg once daily, taken with a meal [see Drug Interactions (7)and Clinical Pharmacology (12.3)].

Note that use of CABENUVA (cabotegravir extended-release injectable suspension; rilpivirine extended-release injectable suspension) with rifabutin is contraindicated. Refer to CABENUVA labeling for additional detail.

3 DOSAGE FORMS AND STRENGTHS

EDURANT 25 mg Film-Coated Tablets

25 mg white to off-white, film-coated, round, biconvex, tablet of 6.4 mm, debossed with "TMC" on one side and "25" on the other side. Each tablet contains 27.5 mg of rilpivirine hydrochloride, which is equivalent to 25 mg of rilpivirine.

EDURANT PED 2.5 mg Tablets for Oral Suspension

2.5 mg white to almost white, round 6.5 mm tablet, debossed with "TMC" on one side and "PED" on the other side. Each tablet for oral suspension contains 2.75 mg of rilpivirine hydrochloride equivalent to 2.5 mg rilpivirine.

4 CONTRAINDICATIONS

EDURANT and EDURANT PED are contraindicated for coadministration with the drugs in Table 2 for which significant decreases in rilpivirine plasma concentrations may occur due to CYP3A enzyme induction or gastric pH increase, which may result in loss of virologic response and possible resistance to EDURANT or EDURANT PED or to the class of NNRTIs [see Drug Interactions (7)and Clinical Pharmacology (12.3)] .

Table 2: Drugs That are Contraindicated with EDURANT and EDURANT PED
Drug Class | Contraindicated Drugs in Class | Clinical Comment
Anticonvulsants | Carbamazepine Oxcarbazepine Phenobarbital Phenytoin | Potential for significant decreases in rilpivirine plasma concentrations due to CYP3A enzyme induction, which may result in loss of virologic response.
Antimycobacterials | Rifampin Rifapentine | Potential for significant decreases in rilpivirine plasma concentrations due to CYP3A enzyme induction, which may result in loss of virologic response.
Glucocorticoid (systemic) | Dexamethasone (more than a single-dose treatment) | Potential for significant decreases in rilpivirine plasma concentrations due to CYP3A enzyme induction, which may result in loss of virologic response.
Herbal Products | St. John's wort (Hypericum perforatum) | Potential for significant decreases in rilpivirine plasma concentrations due to CYP3A enzyme induction, which may result in loss of virologic response.
Proton Pump Inhibitors | e.g., Esomeprazole Lansoprazole Omeprazole Pantoprazole Rabeprazole | Potential for significant decreases in rilpivirine plasma concentrations due to gastric pH increase, which may result in loss of virologic response.

5 WARNINGS AND PRECAUTIONS

5.1 Skin and Hypersensitivity Reactions

Severe skin and hypersensitivity reactions have been reported during the postmarketing experience, including cases of Drug Reaction with Eosinophilia and Systemic Symptoms (DRESS), with rilpivirine-containing regimens. While some skin reactions were accompanied by constitutional symptoms such as fever, other skin reactions were associated with organ dysfunctions, including elevations in hepatic serum biochemistries. During the Phase 3 clinical trials, treatment-related rashes with at least Grade 2 severity were reported in 3% of subjects receiving EDURANT. No Grade 4 rash was reported. Overall, most rashes were Grade 1 or 2 and occurred in the first four to six weeks of therapy [see Adverse Reactions (6.1and 6.2)] . Discontinue EDURANT or EDURANT PED immediately if signs or symptoms of severe skin or hypersensitivity reactions develop, including but not limited to, severe rash or rash accompanied by fever, blisters, mucosal involvement, conjunctivitis, facial edema, angioedema, hepatitis or eosinophilia. Clinical status including laboratory parameters should be monitored and appropriate therapy should be initiated.

5.2 Hepatotoxicity

Hepatic adverse events have been reported in patients receiving a rilpivirine-containing regimen. Patients with underlying hepatitis B or C virus infection, or marked elevations in transaminases prior to treatment may be at increased risk for worsening or development of transaminase elevations with use of EDURANT or EDURANT PED. A few cases of hepatic toxicity have been reported in adult patients receiving a rilpivirine-containing regimen who had no pre-existing hepatic disease or other identifiable risk factors. Appropriate laboratory testing prior to initiating therapy and monitoring for hepatotoxicity during therapy with EDURANT or EDURANT PED is recommended in patients with underlying hepatic disease such as hepatitis B or C virus infection, or in patients with marked elevations in transaminases prior to treatment initiation. Liver enzyme monitoring should also be considered for patients without pre-existing hepatic dysfunction or other risk factors.

5.3 Depressive Disorders

The adverse reaction depressive disorders (depressed mood, depression, dysphoria, major depression, mood altered, negative thoughts, suicide attempt, suicidal ideation) has been reported with EDURANT. Patients with severe depressive symptoms should seek immediate medical evaluation to assess the possibility that the symptoms are related to EDURANT or EDURANT PED, and if so, to determine whether the risks of continued therapy outweigh the benefits.

During the Phase 3 trials in adults (N=1368) through 96 weeks, the incidence of depressive disorders (regardless of causality, severity) reported among EDURANT (n=686) or efavirenz (n=682) was 9% and 8%, respectively. Most events were mild or moderate in severity. The incidence of Grade 3 and 4 depressive disorders (regardless of causality) was 1% for both EDURANT and efavirenz. The incidence of discontinuation due to depressive disorders among EDURANT or efavirenz was 1% in each arm. Suicidal ideation was reported in 4 subjects in each arm while suicide attempt was reported in 2 subjects in the EDURANT arm.

During the Phase 2 trial in pediatric subjects 12 to less than 18 years of age (N=36) receiving EDURANT through 48 weeks, the incidence of depressive disorders (regardless of causality, severity) was 19.4% (7/36). Most events were mild or moderate in severity. The incidence of Grade 3 and 4 depressive disorders (regardless of causality) was 5.6% (2/36). None of the subjects discontinued due to depressive disorders. Suicidal ideation and suicide attempt were reported in 1 subject.

5.4 Risk of Adverse Reactions or Loss of Virologic Response Due to Drug Interactions

The concomitant use of EDURANT or EDURANT PED and other drugs may result in potentially significant drug interactions, some of which may lead to [see Dosage and Administration (2.7), Contraindications (4), and Drug Interactions (7)] :

- Loss of therapeutic effect of EDURANT or EDURANT PED and possible development of resistance.

In healthy subjects, 75 mg once daily and 300 mg once daily (3 times and 12 times the dose in EDURANT) have been shown to prolong the QTc interval of the electrocardiogram. Consider alternatives to EDURANT or EDURANT PED when coadministered with a drug that is known to have a risk of torsade de pointes [see Drug Interactions (7) and Clinical Pharmacology (12.2)] .

See Table 6 for steps to prevent or manage these possible and known significant drug interactions, including dosing recommendations. Consider the potential for drug interactions prior to and during EDURANT or EDURANT PED therapy and review concomitant medications during therapy.

5.5 Immune Reconstitution Syndrome

Immune reconstitution syndrome has been reported in patients treated with combination antiretroviral therapy, including EDURANT. During the initial phase of combination antiretroviral treatment, patients whose immune system responds may develop an inflammatory response to indolent or residual opportunistic infections (such as Mycobacterium avium infection, cytomegalovirus, Pneumocystis jirovecii pneumonia or tuberculosis), which may necessitate further evaluation and treatment.

Autoimmune disorders (such as Graves' disease, polymyositis, Guillain-Barré syndrome, and autoimmune hepatitis) have also been reported to occur in the setting of immune reconstitution; however, the time to onset is more variable, and can occur many months after initiation of treatment.

5.6 Different Formulations Are Not Substitutable

EDURANT and EDURANT PED have differing pharmacokinetic profiles and are not substitutable on a milligram-per-milligram basis. A difference in bioavailability between 1 × 25 mg film-coated tablet and 10 × 2.5 mg tablets for oral suspension was observed; therefore, they are not substitutable [see Clinical Pharmacology (12.3)]. When a pediatric patient weighs 25 kg or greater, they must switch from EDURANT PED tablets for oral suspension to one 25 mg EDURANT tablet daily [see Dosage and Administration (2.3)]. Incorrect dosing of a given formulation may result in underdosing and loss of therapeutic effect and possible development of resistance or possible clinically significant adverse reactions from greater exposure to rilpivirine.

6 ADVERSE REACTIONS

The following adverse reactions are discussed below and in other sections of the labeling:

- Skin and Hypersensitivity Reactions [see Warnings and Precautions (5.1)]
- Hepatotoxicity [see Warnings and Precautions (5.2)]
- Depressive Disorders [see Warnings and Precautions (5.3)]

6.1 Clinical Trials Experience

Because clinical trials are conducted under widely varying conditions, adverse reaction rates observed in the clinical trials of a drug cannot be directly compared to rates in the clinical trials of another drug and may not reflect the rates observed in clinical practice.

Clinical Trials Experience in Adults

The safety assessment is based on the Week 96 pooled data from 1368 patients in the Phase 3 controlled trials TMC278-C209 (ECHO) and TMC278-C215 (THRIVE) in antiretroviral treatment-naïve HIV-1 infected adult patients, 686 of whom received EDURANT (25 mg once daily) [see Clinical Studies (14.1)] . The median duration of exposure for patients in the EDURANT arm and efavirenz arm was 104.3 and 104.1 weeks, respectively. Most adverse reactions occurred in the first 48 weeks of treatment. The proportion of subjects who discontinued treatment with EDURANT or efavirenz due to adverse reaction, regardless of severity, was 2% and 4%, respectively. The most common adverse reactions leading to discontinuation were psychiatric disorders: 10 (1%) subjects in the EDURANT arm and 11 (2%) subjects in the efavirenz arm. Rash led to discontinuation in 1 (<1%) subject in the EDURANT arm and 10 (2%) subjects in the efavirenz arm.

Common Adverse Reactions

Adverse reactions of at least moderate intensity (≥Grade 2) reported in at least 2% of adult subjects are presented in Table 3. Selected laboratory abnormalities are included in Table 4.

Table 3: Selected Adverse Reactions of at Least Moderate Intensity [Intensities are defined as follows: Moderate (discomfort enough to cause interference with usual activity); Severe (incapacitating with inability to work or do usual activity).] (Grades 2–4) Occurring in at Least 2% of Antiretroviral Treatment-Naïve HIV-1 Infected Adult Subjects (Week 96 Analysis)
System Organ Class, Preferred Term, % | Pooled Data from the Phase 3 TMC278-C209 and TMC278-C215 Trials
System Organ Class, Preferred Term, % | EDURANT + BR N=686 | Efavirenz + BR N=682
Gastrointestinal Disorders
Abdominal pain | 2% | 2%
Nausea | 1% | 3%
Vomiting | 1% | 2%
General Disorders and Administration Site Conditions
Fatigue | 2% | 2%
Nervous System Disorders
Headache | 3% | 4%
Dizziness | 1% | 7%
Psychiatric Disorders
Depressive disorders [Includes adverse reactions reported as depressed mood, depression, dysphoria, major depression, mood altered, negative thoughts, suicide attempt, suicide ideation.] | 5% | 4%
Insomnia | 3% | 4%
Abnormal dreams | 2% | 4%
Skin and Subcutaneous Tissue Disorders
Rash | 3% | 11%
N=total number of subjects per treatment group; BR=background regimen

No new adverse reaction terms were identified in adult subjects in the Phase 3 TMC278-C209 and TMC278-C215 trials between 48 weeks and 96 weeks nor in the Phase 2b TMC278-C204 trial through 240 weeks. The incidence of adverse events in the Phase 2b TMC278-C204 trial was similar to the Phase 3 trials through 96 weeks.

Less Common Adverse Reactions

Adverse reactions of at least moderate intensity (≥Grade 2) occurring in less than 2% of antiretroviral treatment-naïve subjects receiving EDURANT are listed below by System Organ Class. Some adverse events have been included because of investigator's assessment of potential causal relationship and were considered serious or have been reported in more than 1 subject treated with EDURANT.

Gastrointestinal Disorders: diarrhea, abdominal discomfort

Hepatobiliary Disorders: cholecystitis, cholelithiasis

Metabolism and Nutrition Disorders: decreased appetite

Nervous System Disorders: somnolence

Psychiatric Disorders: sleep disorders, anxiety

Renal and Urinary Disorders: glomerulonephritis membranous, glomerulonephritis mesangioproliferative, nephrolithiasis

Laboratory Abnormalities in Treatment-Naïve Subjects

The percentage of subjects treated with EDURANT or efavirenz in the Phase 3 trials with selected laboratory abnormalities (Grades 1 to 4), representing worst Grade toxicity are shown in Table 4.

Table 4: Selected Changes in Laboratory Parameters (Grades 1 to 4) Observed in Antiretroviral Treatment-Naïve HIV-1-Infected Adult Subjects (Week 96 Analysis)
Laboratory Parameter Abnormality, (%) | DAIDS Toxicity Range | Pooled Data from the Phase 3 TMC278-C209 and TMC278-C215 Trials
Laboratory Parameter Abnormality, (%) | DAIDS Toxicity Range | EDURANT + BR N=686 | Efavirenz + BR N=682
BIOCHEMISTRY
Increased Creatinine
Grade 1 | ≥1.1–≤1.3 × ULN | 6% | 1%
Grade 2 | >1.3–≤1.8 × ULN | 1% | 1%
Grade 3 | >1.8–≤3.4 × ULN | <1% | 0
Grade 4 | >3.4 × ULN | 0 | <1%
Increased AST
Grade 1 | ≥1.25–≤2.5 × ULN | 16% | 19%
Grade 2 | >2.5–≤5.0 × ULN | 4% | 7%
Grade 3 | >5.0–≤10.0 × ULN | 2% | 2%
Grade 4 | >10.0 × ULN | 1% | 1%
Increased ALT
Grade 1 | ≥1.25–≤2.5 × ULN | 18% | 20%
Grade 2 | >2.5–≤5.0 × ULN | 5% | 7%
Grade 3 | >5.0–≤10.0 × ULN | 1% | 2%
Grade 4 | >10.0 × ULN | 1% | 1%
Increased Total Bilirubin
Grade 1 | ≥1.1–≤1.5 × ULN | 5% | <1%
Grade 2 | >1.5–≤2.5 × ULN | 3% | 1%
Grade 3 | >2.5–≤5.0 × ULN | 1% | <1%
Grade 4 | >5.0 × ULN | 0 | 0
Increased Total Cholesterol (fasted)
Grade 1 | 5.18–6.19 mmol/L 200–239 mg/dL | 17% | 31%
Grade 2 | 6.20–7.77 mmol/L 240–300 mg/dL | 7% | 19%
Grade 3 | >7.77 mmol/L >300 mg/dL | <1% | 3%
Increased LDL Cholesterol (fasted)
Grade 1 | 3.37–4.12 mmol/L 130–159 mg/dL | 14% | 26%
Grade 2 | 4.13–4.90 mmol/L 160–190 mg/dL | 5% | 13%
Grade 3 | ≥4.91 mmol/L ≥191 mg/dL | 1% | 5%
Increased Triglycerides (fasted)
Grade 2 | 5.65–8.48 mmol/L 500–750 mg/dL | 2% | 2%
Grade 3 | 8.49–13.56 mmol/L 751–1,200 mg/dL | 1% | 3%
Grade 4 | >13.56 mmol/L >1,200 mg/dL | 0 | 1%
BR=background regimen; ULN=upper limit of normal
N=number of subjects per treatment group
Note: Percentages were calculated versus the number of subjects in ITT.

Adrenal Function

In the pooled Phase 3 trials, at Week 96, there was an overall mean change from baseline in basal cortisol of -0.69 (-1.12, 0.27) micrograms/dL in the EDURANT group and of -0.02 (-0.48, 0.44) micrograms/dL in the efavirenz group.

In the EDURANT group, 43/588 (7%) of subjects with a normal 250 micrograms ACTH stimulation test at baseline developed an abnormal 250 micrograms ACTH stimulation test (peak cortisol level <18.1 micrograms/dL) during the trial compared to 18/561 (3%) in the efavirenz group. Of the subjects who developed an abnormal 250 micrograms ACTH stimulation test during the trial, fourteen subjects in the EDURANT group and nine subjects in the efavirenz group had an abnormal 250 micrograms ACTH stimulation test at Week 96. Overall, there were no serious adverse events, deaths, or treatment discontinuations that could clearly be attributed to adrenal insufficiency. The clinical significance of the higher abnormal rate of 250 micrograms ACTH stimulation tests in the EDURANT group is not known.

Serum Creatinine

In the pooled Phase 3 trials, an increase in serum creatinine was observed over the 96 weeks of treatment with EDURANT. Most of this increase occurred within the first four weeks of treatment, with a mean change of 0.1 mg/dL (range: -0.3 mg/dL to 0.6 mg/dL) observed after 96 weeks of treatment. In subjects who entered the trial with mild or moderate renal impairment, the serum creatinine increase observed was similar to that seen in subjects with normal renal function. These changes are not considered to be clinically relevant and no subject discontinued treatment due to increases in serum creatinine. Serum creatinine increases occurred regardless of the background N(t)RTI regimen.

Serum Lipids

Changes from baseline in total cholesterol, LDL-cholesterol, HDL-cholesterol and triglycerides are presented in Table 5. The clinical benefit of these findings has not been demonstrated.

Table 5: Lipid Values, Mean Change from Baseline [Excludes subjects who received lipid lowering agents during the treatment period]
 | Pooled Data from the Week 96 Analysis of the Phase 3 TMC278-C209 and TMC278-C215 Trials
 | EDURANT + BR |  |  |  | Efavirenz + BR
 | N | Baseline | Week 96 |  | N | Baseline | Week 96
Mean (95% CI) |  | Mean (mg/dL) | Mean (mg/dL) | Mean Change [The change from baseline is the mean of within-patient changes from baseline for patients with both baseline and Week 96 values] (mg/dL) |  | Mean (mg/dL) | Mean (mg/dL) | Mean Change (mg/dL)
Total Cholesterol (fasted) | 546 | 161 | 166 | 5 | 507 | 160 | 187 | 28
HDL-cholesterol (fasted) | 545 | 41 | 46 | 4 | 505 | 40 | 51 | 11
LDL-cholesterol (fasted) | 543 | 96 | 98 | 1 | 503 | 95 | 109 | 14
Triglycerides (fasted) | 546 | 122 | 116 | -6 | 507 | 130 | 141 | 11
N=number of subjects per treatment group; BR=background regimen

Subjects Co-infected with Hepatitis B and/or Hepatitis C Virus

In subjects co-infected with hepatitis B or C virus receiving EDURANT, the incidence of hepatic enzyme elevation was higher than in subjects receiving EDURANT who were not co-infected. This observation was the same in the efavirenz arm. The pharmacokinetic exposure of rilpivirine in co-infected subjects was comparable to that in subjects without co-infection.

Use in Combination with Cabotegravir

Safety findings from Phase 3/3b trials in adults were similar when EDURANT was administered in combination with VOCABRIA (cabotegravir) or other antiretrovirals. See full prescribing information for VOCABRIA and CABENUVA (cabotegravir extended-release injectable suspension; rilpivirine extended-release injectable suspension) for additional information.

Clinical Trials Experience in Pediatric Patients

Pediatric Population (≥12 to less than 18 years of age)

Trial TMC278-C213 Cohort 1

The safety assessment is based on the Week 48 analysis of the single-arm, open-label, Phase 2 trial, TMC278-C213 Cohort 1, in which 36 antiretroviral treatment-naïve HIV-1 infected patients 12 to less than 18 years of age and weighing at least 32 kg received EDURANT (25 mg once daily) in combination with other antiretroviral agents [see Clinical Studies (14.3)] . The median duration of exposure was 63.5 weeks. There were no patients who discontinued treatment due to adverse reactions. No new adverse reactions were identified compared to those seen in adults.

Adverse reactions were reported in nineteen pediatric subjects (53%). Most adverse reactions were Grade 1 or 2. The most common adverse reactions reported in at least 2 subjects (regardless of severity) include headache (19%), depression (19%), somnolence (14%), nausea (11%), dizziness (8%), abdominal pain (8%), vomiting (6%) and rash (6%).

Observed laboratory abnormalities were comparable to those in adults.

Adrenal Function

In trial TMC278-C213 Cohort 1, at Week 48, the overall mean change from baseline in basal cortisol showed an increase of 1.59 (0.24, 2.93) micrograms/dL.

Six of 30 (20%) subjects with a normal 250 micrograms ACTH stimulation test at baseline developed an abnormal 250 micrograms ACTH stimulation test (peak cortisol level <18.1 micrograms/dL) during the trial. Three of these subjects had an abnormal 250 micrograms ACTH stimulation test at Week 48. Overall, there were no serious adverse events, deaths, or treatment discontinuations that could clearly be attributed to adrenal insufficiency. The clinical significance of the abnormal 250 micrograms ACTH stimulation tests is not known.

Trial 208580 [MOCHA]

Based on data from the Week 16 analysis of the MOCHA trial in 15 adolescents (12 to less than 18 years of age and weighing ≥35 kg) receiving EDURANT (25 mg once daily) in addition to continuing background antiretroviral therapy, the safety profile during the oral lead-in period in adolescents was consistent with the safety profile established with EDURANT in adults.

Pediatric Population (≥2 to less than 12 years of age)

Two clinical trials were conducted in pediatric subjects weighing at least 16 kg (5 to less than 12 years of age). A total of 18 and 26 pediatric subjects were enrolled in Trial TMC278-C213 and Trial TMC278HTX2002, respectively. Overall, the safety data in these pediatric studies were similar to those observed in adults. Safety results from the two trials are summarized below.

Trial TMC278-C213 Cohort 2

Cohort 2 of the single-arm, open-label Phase 2 trial, TMC278-C213 evaluated the safety of the EDURANT and EDURANT PED weight adjusted doses 25, 15 and 12.5 mg once daily in antiretroviral treatment-naïve HIV-1 infected patients (≥6 to <12 years of age and weighing at least 17 kg) [see Clinical Studies (14.4)] . The median duration of exposure for patients in the Week 48 analysis (including post-Week 48 extension) was 69.5 (range 35 to 218) weeks.

All adverse reactions were Grade 1 or 2. Adverse reactions reported in at least 2 subjects, regardless of grading, in Trial TMC278-C213 Cohort 2 were: decreased appetite (3/18, 17%), vomiting (2/18, 11%), ALT increased (2/18, 11%), AST increased (2/18, 11%), and rash (2/18, 11%). No adverse reactions led to discontinuation.

Adrenal Function

In trial TMC278-C213 Cohort 2, basal cortisol at baseline was normal (≥9 μg/dL) for 4/18 subjects, low for 13/18 subjects, and missing for 1/18 subjects.

Among the 4 subjects with normal basal cortisol at baseline, 3 subjects had either normal basal cortisol levels (≥9 μg/dL) or normal cortisol levels 1 hour after ACTH stimulation (≥18.1 μg/dL) throughout the trial and/or at the last available visit (Week 24 and Week 72), and 1 subject had low basal cortisol at the last available assessment (Week 48) and no ACTH stimulation test was performed. Among the 13 subjects with low basal cortisol pre-dose at baseline, 2 subjects had low basal and ACTH stimulated cortisol values throughout the trial, including ACTH stimulated cortisol at baseline before starting treatment with rilpivirine. For both subjects, no adverse events suggestive for adrenal insufficiency were reported. The remaining 11 subjects had normal serum cortisol values after ACTH stimulation at baseline and/or during treatment.

Trial TMC278HTX2002

The single arm, open-label Phase 2 trial, TMC278HTX2002, evaluated the safety of EDURANT and EDURANT PED weight-adjusted doses 25, 15 and 12.5 mg once daily in virologically suppressed HIV-1 infected patients (≥2 to <12 years of age and weighing at least 16 kg). The median duration of exposure for patients in the Week 48 analysis was 48.4 (range 47 to 52) weeks.

All adverse reactions were Grade 1 or 2. Adverse reactions reported in at least 2 subjects, regardless of grading, in Trial TMC278HTX2002 were: vomiting (4/26, 15%), abdominal pain (3/26, 12%), nausea (2/26, 8%), ALT increased (3/26, 12%), AST increased (2/26, 8%), and decreased appetite (2/26, 8%). No adverse reactions led to discontinuation.

Adrenal Function

In trial TMC278HTX2002, 15/26 subjects had either normal basal cortisol (≥9 μg/dL) or normal cortisol 1 hour after ACTH stimulation (≥18.1 μg/dL), 9 had low basal cortisol on Day 1, and in 2 subjects the baseline value was missing.

From the 19 subjects with low basal cortisol at Week 48, in 15 subjects, the Week 48 serum cortisol levels returned to normal (≥248 nmol/L) after repeat serum basal cortisol testing or was normal after ACTH stimulation testing (≥500 nmol/L). In 4 subjects, the serum cortisol levels remained low after repeat serum basal cortisol testing or after ACTH stimulation testing. At Week 48, 6 subjects had normal (basal) cortisol (≥9 ug/dL) and the Week 48 result was not available for 1 subject.

6.2 Postmarketing Experience

Adverse reactions have been identified during postmarketing experience in patients receiving a rilpivirine containing regimen. Because these reactions are reported voluntarily from a population of unknown size, it is not always possible to reliably estimate their frequency or establish a causal relationship to drug exposure.

Renal and Genitourinary Disorders: nephrotic syndrome

Skin and Subcutaneous Tissue Disorders: Severe skin and hypersensitivity reactions including DRESS (Drug Reaction with Eosinophilia and Systemic Symptoms)

7 DRUG INTERACTIONS

Rilpivirine is primarily metabolized by cytochrome P450 (CYP)3A, and drugs that induce or inhibit CYP3A may thus affect the clearance of rilpivirine. Coadministration of EDURANT or EDURANT PED and drugs that induce CYP3A may result in decreased plasma concentrations of rilpivirine and loss of virologic response and possible resistance to rilpivirine or to the class of NNRTIs. Coadministration of EDURANT or EDURANT PED and drugs that inhibit CYP3A may result in increased plasma concentrations of rilpivirine. Coadministration of EDURANT or EDURANT PED with drugs that increase gastric pH may result in decreased plasma concentrations of rilpivirine and loss of virologic response and possible resistance to rilpivirine or to the class of NNRTIs.

EDURANT or EDURANT PED at the recommended doses are not likely to have a clinically relevant effect on the exposure of drugs metabolized by CYP enzymes.

Table 6 shows the established and other potentially significant drug interactions based on which alterations in dose or regimen of EDURANT or EDURANT PED and/or coadministered drug may be recommended. Drugs that are not recommended for coadministration with EDURANT or EDURANT PED are also included in Table 6 [see Dosage and Administration (2), Contraindications (4), and Clinical Pharmacology (12.3)].

Table 6: Established and Other Potentially Significant Drug Interactions: Alterations in Dose or Regimen May Be Recommended Based on Drug Interaction Studies or Predicted Interaction [see Clinical Pharmacology (12.3)]
Concomitant Drug Class: Drug Name | Effect on Concentration of Rilpivirine or Concomitant Drug | Clinical Comment
Antacids: antacids (e.g., aluminum or magnesium hydroxide, calcium carbonate) | ↔ rilpivirine (antacids taken at least 2 hours before or at least 4 hours after rilpivirine) | The combination of EDURANT or EDURANT PED and antacids should be used with caution as coadministration may cause significant decreases in rilpivirine plasma concentrations (increase in gastric pH). Antacids should only be administered either at least 2 hours before or at least 4 hours after EDURANT or EDURANT PED.
 | ↓ rilpivirine (concomitant intake)
Anticonvulsants: carbamazepine oxcarbazepine phenobarbital phenytoin | ↓ rilpivirine | Coadministration is contraindicated with EDURANT or EDURANT PED [see Contraindications (4)] .
Antimycobacterials: rifampin rifapentine | ↓ rilpivirine | Coadministration is contraindicated with EDURANT or EDURANT PED [see Contraindications (4)] .
Antimycobacterials: rifabutin [The interaction between EDURANT and the drug was evaluated in a clinical study. All other drug-drug interactions shown are predicted.] | ↓ rilpivirine | Concomitant use of EDURANT with rifabutin may cause a decrease in the plasma concentrations of rilpivirine (induction of CYP3A enzymes). Throughout coadministration of EDURANT with rifabutin, the EDURANT dose should be increased from 25 mg once daily to 50 mg once daily. When rifabutin coadministration is stopped, the EDURANT dose should be decreased to 25 mg once daily.
Azole Antifungal Agents: fluconazole itraconazole ketoconazole [This interaction study has been performed with a dose higher than the recommended dose for EDURANT assessing the maximal effect on the coadministered drug. The dosing recommendation is applicable to the recommended doses of EDURANT once daily.] posaconazole voriconazole | ↑ rilpivirine ↓ ketoconazole | Concomitant use of EDURANT or EDURANT PED with azole antifungal agents may cause an increase in the plasma concentrations of rilpivirine (inhibition of CYP3A enzymes). No rilpivirine dose adjustment is required when EDURANT or EDURANT PED is coadministered with azole antifungal agents. Clinically monitor for breakthrough fungal infections when azole antifungals are coadministered with EDURANT or EDURANT PED.
Glucocorticoid (systemic): dexamethasone (more than a single-dose treatment) | ↓ rilpivirine | Coadministration is contraindicated with EDURANT or EDURANT PED [see Contraindications (4)] .
H2-Receptor Antagonists: cimetidine famotidine nizatidine ranitidine | ↔ rilpivirine (famotidine taken 12 hours before rilpivirine or 4 hours after rilpivirine) | The combination of EDURANT or EDURANT PED and H2-receptor antagonists should be used with caution as coadministration may cause significant decreases in rilpivirine plasma concentrations (increase in gastric pH). H2-receptor antagonists should only be administered at least 12 hours before or at least 4 hours after EDURANT or EDURANT PED.
 | ↓ rilpivirine (famotidine taken 2 hours before rilpivirine)
Herbal Products: St. John's wort (Hypericum perforatum) | ↓ rilpivirine | Coadministration is contraindicated with EDURANT or EDURANT PED [see Contraindications (4)] .
HIV-Antiviral Agents: Non-nucleoside Reverse Transcriptase Inhibitors (NNRTIs)
NNRTI (delavirdine) | ↑ rilpivirine ↔ delavirdine | It is not recommended to coadminister EDURANT or EDURANT PED with delavirdine and other NNRTIs.
Other NNRTIs (efavirenz, etravirine, nevirapine) | ↓ rilpivirine ↔ other NNRTIs
HIV-Antiviral Agents: Nucleoside Reverse Transcriptase Inhibitors (NRTIs)
didanosine | ↔ rilpivirine ↔ didanosine | No dose adjustment is required when EDURANT or EDURANT PED is coadministered with didanosine. Didanosine is to be administered on an empty stomach and at least two hours before or at least four hours after EDURANT or EDURANT PED (which should be administered with a meal).
HIV-Antiviral Agents: Protease Inhibitors (PIs)-Boosted (i.e., with coadministration of low-dose ritonavir) or Unboosted (i.e., without coadministration of low-dose ritonavir)
darunavir/ritonavir | ↑ rilpivirine ↔ boosted darunavir | Concomitant use of EDURANT or EDURANT PED with darunavir/ritonavir may cause an increase in the plasma concentrations of rilpivirine (inhibition of CYP3A enzymes). No dose adjustment is required when EDURANT or EDURANT PED is coadministered with darunavir/ritonavir.
Lopinavir/ritonavir | ↑ rilpivirine ↔ boosted lopinavir | Concomitant use of EDURANT or EDURANT PED with lopinavir/ritonavir may cause an increase in the plasma concentrations of rilpivirine (inhibition of CYP3A enzymes). No dose adjustment is required when EDURANT or EDURANT PED is coadministered with lopinavir/ritonavir.
Other boosted PIs (atazanavir/ritonavir, fosamprenavir/ritonavir, saquinavir/ritonavir, tipranavir/ritonavir) | ↑ rilpivirine ↔ boosted PI | Concomitant use of EDURANT or EDURANT PED with boosted PIs may cause an increase in the plasma concentrations of rilpivirine (inhibition of CYP3A enzymes). EDURANT or EDURANT PED is not expected to affect the plasma concentrations of coadministered PIs.
Unboosted PIs (atazanavir, fosamprenavir, indinavir, nelfinavir) | ↑ rilpivirine ↔ unboosted PI | Concomitant use of EDURANT or EDURANT PED with unboosted PIs may cause an increase in the plasma concentrations of rilpivirine (inhibition of CYP3A enzymes). EDURANT or EDURANT PED is not expected to affect the plasma concentrations of coadministered PIs.
Macrolide or ketolide antibiotics: azithromycin clarithromycin erythromycin | ↑ rilpivirine ↔ azithromycin ↔ clarithromycin ↔ erythromycin | Macrolides are expected to increase concentrations of rilpivirine and are associated with a risk of Torsade de Pointes [Warnings and Precautions (5.4)].Where possible, consider alternatives, such as azithromycin, which increases rilpivirine concentrations less than other macrolides.
Narcotic Analgesics: methadone | ↓ R(-) methadone ↓ S(+) methadone | No dose adjustments are required when initiating coadministration of methadone with EDURANT or EDURANT PED. However, clinical monitoring is recommended as methadone maintenance therapy may need to be adjusted in some patients.
Proton Pump Inhibitors: e.g., esomeprazole lansoprazole omeprazole pantoprazole rabeprazole | ↓ rilpivirine | Coadministration is contraindicated with EDURANT or EDURANT PED [see Contraindications (4)] .
↑=increase, ↓=decrease, ↔=no change

In addition to the drugs included in Table 6, the interaction between EDURANT and the following drugs was evaluated in clinical studies and no dose adjustment is needed for either drug [see Clinical Pharmacology (12.3)] : acetaminophen, atorvastatin, chlorzoxazone, cabotegravir, ethinylestradiol, norethindrone, raltegravir, sildenafil, simeprevir and tenofovir disoproxil fumarate. Rilpivirine did not have a clinically significant effect on the pharmacokinetics of digoxin or metformin. No clinically relevant drug-drug interaction is expected when EDURANT or EDURANT PED is coadministered with maraviroc, ribavirin or the NRTIs abacavir, emtricitabine, lamivudine, stavudine and zidovudine.

QT Prolonging Drugs

There is limited information available on the potential for a pharmacodynamic interaction between rilpivirine and drugs that prolong the QTc interval of the electrocardiogram. In a study of healthy subjects, 75 mg once daily and 300 mg once daily (3 times and 12 times the dose in EDURANT) have been shown to prolong the QTc interval of the electrocardiogram [see Clinical Pharmacology (12.2)] . Consider alternatives to EDURANT when coadministered with a drug with a known risk of torsade de pointes.

8 USE IN SPECIFIC POPULATIONS

8.1 Pregnancy

Pregnancy Exposure Registry

There is a pregnancy exposure registry that monitors pregnancy outcomes in women exposed to EDURANT during pregnancy. Healthcare providers are encouraged to register patients by calling the Antiretroviral Pregnancy Registry (APR) 1-800-258-4263.

Risk Summary

Available data from the APR show no difference in the overall risk of birth defects for rilpivirine compared with the background rate for major birth defects of 2.7% in the Metropolitan Atlanta Congenital Defects Program (MACDP) reference population (see Data) . The rate of miscarriage is not reported in the APR. The estimated background rate of miscarriage in clinically recognized pregnancies in the U.S. general population is 15% to 20%. The background risk for major birth defects and miscarriage for the indicated population is unknown. Methodologic limitations of the APR include the use of MACDP as the external comparator group. The MACDP population is not disease-specific, evaluates women and infants from a limited geographic area, and does not include outcomes for births that occurred at <20 weeks gestation. In a clinical trial, total rilpivirine exposures were generally lower during pregnancy compared to the postpartum period (see Data) .

In animal reproduction studies, no adverse developmental outcomes were observed when rilpivirine was administered orally at exposures up to 15 (rats) and 70 (rabbits) times the exposure in humans (≥12 years of age and weighing at least 32 kg) at the recommended dose of 25 mg once daily (see Data) .

Clinical Considerations

Dosing During Pregnancy and the Postpartum Period

Based on the experience of HIV-1-infected pregnant women who completed a clinical trial through the postpartum period with a rilpivirine-based regimen, no dose adjustments are required for pregnant patients who are already on a stable EDURANT regimen prior to pregnancy and who are virologically suppressed (HIV-1 RNA less than 50 copies per mL) [see Dosage and Administration (2.5)]. Lower exposures of rilpivirine were observed during pregnancy, therefore viral load should be monitored closely [see Clinical Pharmacology (12.3)] .

Data

Human Data

Based on prospective reports to the APR of over 550 exposures to rilpivirine during the first trimester of pregnancy resulting in live births, there was no significant difference between the overall risk of birth defects with rilpivirine compared to the background birth defect rate of 2.7% in the U.S. reference population of the MACDP. The prevalence of birth defects in live births was 1.4% (95% CI: 0.6% to 2.8%) and 1.5% (95% CI: 0.3% to 4.3%) following first and second/third trimester exposure, respectively, to rilpivirine-containing regimens.

Rilpivirine in combination with a background regimen was evaluated in a clinical trial of 19 HIV-1 infected pregnant women during the second and third trimesters and postpartum. Each of the women were on a rilpivirine-based regimen at the time of enrollment. Twelve subjects completed the trial through the postpartum period (6–12 weeks after delivery) and pregnancy outcomes are missing for six subjects. The exposure (C0hand AUC) of total rilpivirine was approximately 30 to 40% lower during pregnancy compared with postpartum (6 to 12 weeks). The protein binding of rilpivirine was similar (>99%) during second trimester, third trimester, and postpartum period. One subject discontinued the trial following spontaneous termination of the pregnancy at 25 weeks gestation due to suspected premature rupture of membranes. Among the 12 subjects who were virologically suppressed at baseline (less than 50 copies/mL), virologic response was preserved in 10 subjects (83.3%) through the third trimester visit and in 9 subjects (75%) through the 6–12 week postpartum visit. Virologic outcomes during the third trimester visit were missing for two subjects who were withdrawn (one subject was nonadherent to the study drug and one subject withdrew consent). Among the 10 infants with HIV test results available, born to 10 HIV-infected pregnant women, all had test results that were negative for HIV-1 at the time of delivery and up to 16 weeks postpartum. All 10 infants received antiretroviral prophylactic treatment with zidovudine. Rilpivirine was well tolerated during pregnancy and postpartum. There were no new safety findings compared with the known safety profile of rilpivirine in HIV–1-infected adults.

Animal Data

Rilpivirine was administered orally to pregnant rats (40, 120, or 400 mg per kg per day) and rabbits (5, 10, or 20 mg per kg per day) through organogenesis (on gestation Days 6 through 17, and 6 through 19, respectively). No significant toxicological effects were observed in embryo-fetal toxicity studies performed with rilpivirine in rats and rabbits at exposures 15 (rats) and 70 (rabbits) times higher than the exposure in humans (≥12 years of age and weighing >32 kg) at the recommended dose of 25 mg once daily. In a pre- and postnatal development study, rilpivirine was administered orally up to 400 mg/kg/day through lactation. No adverse effects were noted in the offspring at maternal exposures up to 63 times the exposure in humans (≥12 years of age and weighing >32 kg) at the recommended dose of 25 mg daily.

8.2 Lactation

Risk Summary

Based on limited data after oral administration, rilpivirine is present in human breast milk. The data do not allow determination of the amount of rilpivirine that is transferred to milk. There are no data on the effects on a breastfed infant, or the effects on milk production. Rilpivirine is present in rat milk (see Data) . Potential risks of breastfeeding include: (1) HIV transmission (in HIV-negative infants), (2) developing viral resistance (in HIV-positive infants), and (3) adverse reactions in a breastfed infant similar to those seen in adults.

Data

Animal Data

Animal lactation studies with rilpivirine have not been conducted. However, rilpivirine was detected in the plasma of nursing pups on lactation day 7 in the rat pre- and postnatal development study.

8.4 Pediatric Use

The safety and effectiveness of EDURANT and EDURANT PED has been established for the treatment of HIV-1 infection in treatment-naïve pediatric patients 2 years of age and older and weighing at least 14 kg. Use of EDURANT or EDURANT PED in this population is supported by three trials: TMC278-C213, TMC278HTX2002 and MOCHA.

Trial TMC278-C213

TMC278-C213 was a single arm, open-label, Phase 2 trial in antiretroviral treatment-naïve HIV-1 infected pediatric subjects, and was divided into two Cohorts.

- Cohort 1 evaluated the safety, efficacy and pharmacokinetics of EDURANT and enrolled 36 children aged 12 to less than 18 years of age and weighing at least 32 kg [see Adverse Reactions (6.1), Clinical Pharmacology (12.3), and Clinical Studies (14.3)] .
- Cohort 2 evaluated the safety, tolerability, antiviral activity and pharmacokinetics of EDURANT and EDURANT PED weight-adjusted doses 25, 15 and 12.5 mg daily, and enrolled 18 children aged 6 to less than 12 years of age and weighing at least 17 kg [see Adverse Reactions (6.1), Clinical Pharmacology (12.3), and Clinical Studies (14.4)] .

Trial TMC278HTX2002

The safety, tolerability, antiviral activity and pharmacokinetics of EDURANT and EDURANT PED weight-adjusted doses 25, 15 and 12.5 mg daily was evaluated in a single-arm, open-label Phase 2 trial in 26 HIV-1 infected pediatric subjects 2 to less than 12 years of age and weighing at least 16 kg. Trial TMC278HTX2002 supports the safety and effectiveness of EDURANT and EDURANT PED in treatment-naïve HIV-1 infected pediatric patients 2 to less than 6 years of age [see Adverse Reactions (6.1) and Clinical Pharmacology (12.3)].

MOCHA Trial (NCT03497676)

The safety, tolerability, and pharmacokinetics of oral and injectable cabotegravir and oral and injectable rilpivirine are being assessed in an ongoing Phase 1/2 multicenter, open-label, non- comparative study, MOCHA (IMPAACT 2017) [see Adverse Reactions (6.1)] . Refer to the VOCABRIA and CABENUVA prescribing information for additional information when EDURANT is used in combination with cabotegravir.

The safety and effectivness of EDURANT in these pediatric subjects were similar to that seen in adults, and there were no significant changes on rilpivirine exposures [see Adverse Reactions (6.1), Clinical Pharmacology (12.3), and Clinical Studies (14)].

Safety and effectiveness in pediatric patients less than 2 years of age or weighing less than 14 kg have not been established. Treatment with EDURANT PED is not recommended in pediatric patients less than 2 years of age or weighing below 14 kg [see Warnings and Precautions (5.6)] .

8.5 Geriatric Use

Clinical studies of EDURANT did not include sufficient numbers of subjects aged 65 and over to determine whether they respond differently from younger subjects. In general, caution should be exercised in the administration and monitoring of EDURANT in elderly patients reflecting the greater frequency of decreased renal and hepatic function, and of concomitant disease or other drug therapy.

8.6 Renal Impairment

No dose adjustment of EDURANT or EDURANT PED is required in patients with mild or moderate renal impairment. However, in patients with severe renal impairment or end-stage renal disease, EDURANT or EDURANT PED should be used with caution and with increased monitoring for adverse effects, as rilpivirine concentrations may be increased due to alteration of drug absorption, distribution, and metabolism secondary to renal dysfunction. As rilpivirine is highly bound to plasma proteins, it is unlikely that it will be significantly removed by hemodialysis or peritoneal dialysis [see Clinical Pharmacology (12.3)] .

8.7 Hepatic Impairment

No dosage adjustment of EDURANT or EDURANT PED is required in patients with mild (Child-Pugh Class A) or moderate (Child-Pugh Class B) hepatic impairment. EDURANT and EDURANT PED have not been studied in patients with severe hepatic impairment (Child-Pugh Class C) [see Clinical Pharmacology (12.3)] .

10 OVERDOSAGE

There is no specific antidote for overdose with EDURANT or EDURANT PED. Human experience of overdose with EDURANT or EDURANT PED is limited. Treatment of overdose with EDURANT or EDURANT PED consists of general supportive measures including monitoring of vital signs and ECG (QT interval) as well as observation of the clinical status of the patient. It is advisable to contact a poison control center to obtain the latest recommendations for the management of an overdose. Since rilpivirine is highly bound to plasma protein, dialysis is unlikely to result in significant removal of the active substance.

11 DESCRIPTION

EDURANT® (rilpivirine) is a non-nucleoside reverse transcriptase inhibitor (NNRTI) of human immunodeficiency virus type 1 (HIV-1).

The chemical name for rilpivirine hydrochloride is 4-[[4-[[4-[(E)-2-cyanoethenyl]-2,6-dimethylphenyl]amino]-2-pyrimidinyl]amino]benzonitrile monohydrochloride. Its molecular formula is C22H18N6∙ HCl and its molecular weight is 402.88. Rilpivirine hydrochloride has the following structural formula:

Rilpivirine hydrochloride is a white to almost white powder. Rilpivirine hydrochloride is practically insoluble in water over a wide pH range.

EDURANT 25 mg tablets are available as a white to off-white, film-coated, round, biconvex, 6.4 mm tablet for oral administration. Each tablet contains 27.5 mg of rilpivirine hydrochloride, which is equivalent to 25 mg of rilpivirine. Each EDURANT 25 mg tablet also contains the inactive ingredients croscarmellose sodium, lactose monohydrate, magnesium stearate, polysorbate 20, povidone K30 and silicified microcrystalline cellulose. The tablet coating contains hypromellose 2910 6 mPa.s, lactose monohydrate, PEG 3000, titanium dioxide and triacetin.

EDURANT PED 2.5 mg tablets for oral suspension are available as white to almost white, round 6.5 mm tablet, debossed with "TMC" on one side and "PED" on the other side. Each tablet for oral suspension contains 2.75 mg of rilpivirine hydrochloride equivalent to 2.5 mg rilpivirine. Each tablet for oral suspension also contains the inactive ingredients croscarmellose sodium, lactose monohydrate, mannitol, microcrystalline cellulose, polysorbate 20, povidone K30, sodium lauryl sulfate and sodium stearyl fumarate.

12 CLINICAL PHARMACOLOGY

12.1 Mechanism of Action

Rilpivirine is an antiviral drug [see Microbiology (12.4)] .

12.2 Pharmacodynamics

Effects on Electrocardiogram

The effect of EDURANT at the recommended dose of 25 mg once daily on the QTcF interval was evaluated in a randomized, placebo and active (moxifloxacin 400 mg once daily) controlled crossover study in 60 healthy adults, with 13 measurements over 24 hours at steady state. The maximum mean time-matched (95% upper confidence bound) differences in QTcF interval from placebo after baseline-correction was 2.0 (5.0) milliseconds (i.e., below the threshold of clinical concern).

When doses of 75 mg once daily and 300 mg once daily of EDURANT (3 times and 12 times the dose in EDURANT) were studied in healthy adults, the maximum mean time-matched (95% upper confidence bound) differences in QTcF interval from placebo after baseline-correction were 10.7 (15.3) and 23.3 (28.4) milliseconds, respectively. Steady-state administration of EDURANT 75 mg once daily and 300 mg once daily resulted in a mean steady-state Cmaxapproximately 2.6-fold and 6.7-fold, respectively, higher than the mean Cmaxobserved with the recommended 25 mg once daily dose of EDURANT [see Warnings and Precautions (5.4)] .

12.3 Pharmacokinetics

Pharmacokinetics in Adults

The pharmacokinetic properties of rilpivirine have been evaluated in adult healthy subjects and in adult antiretroviral treatment-naïve HIV-1-infected subjects. Exposure to rilpivirine was generally lower in HIV-1 infected subjects than in healthy subjects.

Table 7: Pharmacokinetic Estimates of Rilpivirine 25 mg Once Daily in Antiretroviral Treatment-Naïve HIV-1-Infected Adult Subjects (Pooled Data from Phase 3 Trials through Week 96)
Parameter | Rilpivirine 25 mg once daily N=679
AUC24h(ng∙h/mL)
Mean±Standard Deviation | 2235±851
Median (Range) | 2096 (198 – 7307)
C0h(ng/mL)
Mean±Standard Deviation | 79±35
Median (Range) | 73 (2 – 288)

Absorption and Bioavailability

After oral administration, the maximum plasma concentration of rilpivirine is generally achieved within 4–5 hours. The absolute bioavailability of EDURANT and EDURANT PED is unknown.

Effects of Food on Oral Absorption

The exposure to rilpivirine was approximately 40% lower when EDURANT was taken in a fasted condition as compared to a normal caloric meal (533 kcal) or high-fat high-caloric meal (928 kcal). When EDURANT was taken with only a protein-rich nutritional drink, exposures were 50% lower than when taken with a meal.

Administration of the EDURANT PED 2.5 mg tablets dispersed in drinking water in fasted conditions or after yogurt consumption resulted in a 31% and 28% lower exposure, respectively, compared to administration in fed conditions (a meal containing 533 kcal) in adults.

Distribution

Rilpivirine is approximately 99.7% bound to plasma proteins in vitro, primarily to albumin. The distribution of rilpivirine into compartments other than plasma (e.g., cerebrospinal fluid, genital tract secretions) has not been evaluated in humans.

Metabolism

In vitro experiments indicate that rilpivirine primarily undergoes oxidative metabolism mediated by the cytochrome P450 (CYP) 3A system.

Elimination

The terminal elimination half-life of rilpivirine is approximately 50 hours. After single dose oral administration of^14C-rilpivirine, on average 85% and 6.1% of the radioactivity could be retrieved in feces and urine, respectively. In feces, unchanged rilpivirine accounted for on average 25% of the administered dose. Only trace amounts of unchanged rilpivirine (<1% of dose) were detected in urine.

Specific Populations

Pregnancy and Postpartum

The exposure (C0hand AUC24h) to total rilpivirine after intake of rilpivirine 25 mg once daily as part of an antiretroviral regimen was 30 to 40% lower during pregnancy (similar for the second and third trimester), compared with postpartum (see Table 8). However, the exposure during pregnancy was not significantly different from exposures obtained in Phase 3 trials. Based on the exposure-response relationship for rilpivirine, this decrease is not considered clinically relevant in patients who are virollogically suppressed. The protein binding of rilpivirine was similar (>99%) during the second trimester, third trimester, and postpartum.

Table 8: Pharmacokinetic Results of Total Rilpivirine After Administration of Rilpivirine 25 mg Once Daily as Part of an Antiretroviral Regimen, During the 2nd Trimester of Pregnancy, the 3rd Trimester of Pregnancy and Postpartum
Pharmacokinetics of total rilpivirine (mean ± SD, tmax: median [range]) | Postpartum (6–12 Weeks) (n=11) | 2nd Trimester of pregnancy (n=15) | 3rd Trimester of pregnancy (n=13)
C0h, ng/mL | 111±69.2 | 65.0±23.9 | 63.5±26.2
Cmin, ng/mL | 84.0±58.8 | 54.3±25.8 | 52.9±24.4
Cmax, ng/mL | 167±101 | 121±45.9 | 123±47.5
tmax, h | 4.00 (2.03–25.08) | 4.00 (1.00–9.00) | 4.00 (2.00–24.93)
AUC24h, ng.h/mL | 2714±1535 | 1792±711 | 1762±662

Pediatric Patients

The pharmacokinetics of rilpivirine in HIV-1 infected pediatric patients 2 to less than 18 years of age and weighing at least 16 kg receiving the recommended weight-based dosing regimen of EDURANT and EDURANT PED were comparable or slightly higher than those obtained in treatment-naïve HIV-1 infected adult patients (see Table 9 and Table 10).

Table 9: Pharmacokinetic Estimates of Rilpivirine After Administration of the Recommended Daily Oral Dosing Regimen in Pediatric Patients ≥6 to <18 Years (Trial TMC278-C213) [The 12.5 mg and 15 mg doses were administered as 5 and 6 dispersed 2.5 mg tablets, respectively. The 25 mg dose was administered as one 25 mg tablet. Mean rilpivirine exposure was approximately 40% higher in TMC278HTX2002 compared to TMC278-C213]
Pharmacokinetics of rilpivirine [Individual data when N=2] Mean±SD Median (range) | 12.5 mg once daily <20 kg | 15 mg once daily ≥20 to <25 kg | 25 mg once daily ≥25 kg
N | 2 | 2 | 44
AUC24h(ng.h/mL) | 1974, 2707 NA (1974 – 2707) | 1912, 2477 NA (1912 – 2477) | 2536±979 2413 (973 – 4848)
C0h(ng/mL) | 68.1, 86.7 NA (68.1 – 86.7) | 48.3, 80.0 NA (48.3 – 80.0) | 87.0±34.5 82.7 (27.8 – 171)
NA = not applicable

Table 10: Pharmacokinetic Estimates of Rilpivirine After Administration of the Recommended Daily Oral Dosing Regimen in Pediatric Patients ≥2 to <18 Years (Trial TMC278HTX2002) [The 12.5 mg and 15 mg doses were administered as 5 and 6 dispersed 2.5 mg tablets, respectively. The 25 mg dose was administered as one 25 mg tablet. Mean rilpivirine exposure was approximately 40% higher in TMC278HTX2002 compared to TMC278-C213]
Pharmacokinetics of rilpivirine [Individual data when N=2] Mean±SD Median (range) | 12.5 mg once daily ≥10 to <20 kg | 15 mg once daily ≥20 to <25 kg | 25 mg once daily ≥25 kg
N | 2 | 5 | 18
AUC24h(ng.h/mL) | 4375, 5057 NA (4375 – 5057) | 3541±949 3112 (2689 – 4947) | 4195±1056 4016 (2732 – 6260)
C0h(ng/mL) | 151, 163 NA (151 – 163) | 112±39.8 91.8 (73.7 – 172) | 134±38.7 121 (78.9 – 220)
NA = not applicable

Renal Impairment

Pharmacokinetic analysis indicated that rilpivirine exposure was similar in HIV-1 infected subjects with mild renal impairment relative to HIV-1 infected subjects with normal renal function. No dose adjustment is required in patients with mild renal impairment. There is limited or no information regarding the pharmacokinetics of rilpivirine in patients with moderate or severe renal impairment or in patients with end-stage renal disease, and rilpivirine concentrations may be increased due to alteration of drug absorption, distribution, and metabolism secondary to renal dysfunction. The potential impact is not expected to be of clinical relevance for HIV-1-infected subjects with moderate renal impairment, and no dose adjustment is required in these patients. Rilpivirine should be used with caution and with increased monitoring for adverse effects in patients with severe renal impairment or end-stage renal disease. As rilpivirine is highly bound to plasma proteins, it is unlikely that it will be significantly removed by hemodialysis or peritoneal dialysis [see Use in Specific Populations (8.6)] .

Hepatic Impairment

Rilpivirine is primarily metabolized and eliminated by the liver. In a study comparing 8 subjects with mild hepatic impairment (Child-Pugh score A) to 8 matched controls, and 8 subjects with moderate hepatic impairment (Child-Pugh score B) to 8 matched controls, the multiple dose exposure of rilpivirine was 47% higher in subjects with mild hepatic impairment and 5% higher in subjects with moderate hepatic impairment. EDURANT has not been studied in subjects with severe hepatic impairment (Child-Pugh score C) [see Use in Specific Populations (8.7)] .

Sex, Race, Hepatitis B and/or Hepatitis C Virus Co-infection

No clinically relevant differences in the pharmacokinetics of rilpivirine have been observed between sex, race and patients with hepatitis B and/or C-virus co-infection.

Drug Interactions

[see Contraindications (4)and Drug Interactions (7)].

Rilpivirine is primarily metabolized by cytochrome P450 (CYP)3A, and drugs that induce or inhibit CYP3A may thus affect the clearance of rilpivirine. Coadministration of EDURANT or EDURANT PED and drugs that induce CYP3A may result in decreased plasma concentrations of rilpivirine and loss of virologic response and possible resistance. Coadministration of EDURANT and EDURANT PED and drugs that inhibit CYP3A may result in increased plasma concentrations of rilpivirine. Coadministration of EDURANT and EDURANT PED with drugs that increase gastric pH may result in decreased plasma concentrations of rilpivirine and loss of virologic response and possible resistance to rilpivirine and to the class of NNRTIs.

EDURANT and EDURANT PED at the recommended doses are not likely to have a clinically relevant effect on the exposure of medicinal products metabolized by CYP enzymes.

Drug interaction studies were performed with EDURANT and other drugs likely to be coadministered or commonly used as probes for pharmacokinetic interactions. The effects of coadministration of other drugs on the Cmax, AUC, and Cminvalues of rilpivirine are summarized in Table 11 (effect of other drugs on EDURANT). The effect of coadministration of EDURANT on the Cmax, AUC, and Cminvalues of other drugs are summarized in Table 12 (effect of EDURANT on other drugs). [For information regarding clinical recommendations, see Drug Interactions (7)].

Table 11: Drug Interactions: Pharmacokinetic Parameters for Rilpivirine in the Presence of Coadministered Drugs
Coadministered Drug | Dose/Schedule |  | N | Mean Ratio of Rilpivirine Pharmacokinetic Parameters With/Without Coadministered Drug (90% CI); No Effect=1.00
Coadministered Drug | Coadministered Drug | Rilpivirine | N | Cmax | AUC | Cmin
Coadministration With HIV Protease Inhibitors (PIs)
Darunavir/ritonavir | 800/100 mg q.d. | 150 mg q.d. [This interaction study has been performed with a dose higher than the recommended dose for EDURANT assessing the maximal effect on the coadministered drug.] | 14 | 1.79 (1.56–2.06) | 2.30 (1.98–2.67) | 2.78 (2.39–3.24)
Lopinavir/ritonavir (soft gel capsule) | 400/100 mg b.i.d. | 150 mg q.d. | 15 | 1.29 (1.18–1.40) | 1.52 (1.36–1.70) | 1.74 (1.46–2.08)
Coadministration With HIV Nucleoside or Nucleotide Reverse Transcriptase Inhibitors (NRTIs/N[t]RTIs)
Didanosine | 400 mg q.d. delayed release capsules taken 2 hours before rilpivirine | 150 mg q.d. | 21 | 1.00 (0.90–1.10) | 1.00 (0.95–1.06) | 1.00 (0.92–1.09)
Tenofovir disoproxil fumarate | 300 mg q.d. | 150 mg q.d. | 16 | 0.96 (0.81–1.13) | 1.01 (0.87–1.18) | 0.99 (0.83–1.16)
Coadministration With HIV Integrase Strand Transfer Inhibitors
Cabotegravir | 30 mg q.d. | 25 mg q.d. | 11 | 0.96 (0.85–1.09) | 0.99 (0.89–1.09) | 0.92 (0.79–1.07)
Raltegravir | 400 mg b.i.d. | 25 mg q.d. | 23 | 1.12 (1.04–1.20) | 1.12 (1.05–1.19) | 1.03 (0.96–1.12)
Coadministration With other Antivirals
Simeprevir | 150 mg q.d. | 25 mg q.d. | 23 | 1.04 (0.95–1.13) | 1.12 (1.05–1.19) | 1.25 (1.16–1.35)
Coadministration With Drugs other than Antiretrovirals
Acetaminophen | 500 mg single dose | 150 mg q.d. | 16 | 1.09 (1.01–1.18) | 1.16 (1.10–1.22) | 1.26 (1.16–1.38)
Atorvastatin | 40 mg q.d. | 150 mg q.d. | 16 | 0.91 (0.79–1.06) | 0.90 (0.81–0.99) | 0.90 (0.84–0.96)
Chlorzoxazone | 500 mg single dose taken 2 hours after rilpivirine | 150 mg q.d. | 16 | 1.17 (1.08–1.27) | 1.25 (1.16–1.35) | 1.18 (1.09–1.28)
Ethinylestradiol/Norethindrone | 0.035 mg q.d./ 1 mg q.d. | 25 mg q.d. | 15 | ↔ [Comparison based on historic controls] | ↔ | ↔
Famotidine | 40 mg single dose taken 12 hours before rilpivirine | 150 mg single dose | 24 | 0.99 (0.84–1.16) | 0.91 (0.78–1.07) | N.A.
Famotidine | 40 mg single dose taken 2 hours before rilpivirine | 150 mg single dose | 23 | 0.15 (0.12–0.19) | 0.24 (0.20–0.28) | N.A.
Famotidine | 40 mg single dose taken 4 hours after rilpivirine | 150 mg single dose | 24 | 1.21 (1.06–1.39) | 1.13 (1.01–1.27) | N.A.
Ketoconazole | 400 mg q.d. | 150 mg q.d. | 15 | 1.30 (1.13–1.48) | 1.49 (1.31–1.70) | 1.76 (1.57–1.97)
Methadone | 60–100 mg q.d., individualized dose | 25 mg q.d. | 12 | ↔ | ↔ | ↔
Omeprazole | 20 mg q.d. | 150 mg q.d. | 16 | 0.60 (0.48–0.73) | 0.60 (0.51–0.71) | 0.67 (0.58–0.78)
Rifabutin | 300 mg q.d. | 25 mg q.d. | 18 | 0.69 (0.62–0.76) | 0.58 (0.52–0.65) | 0.52 (0.46–0.59)
Rifabutin | 300 mg q.d. | 50 mg q.d. | 18 | 1.43 (1.30–1.56) | 1.16 (1.06–1.26) | 0.93 (0.85–1.01)
 |  |  |  | (reference arm for comparison was 25 mg q.d. rilpivirine administered alone)
Rifampin | 600 mg q.d. | 150 mg q.d. | 16 | 0.31 (0.27–0.36) | 0.20 (0.18–0.23) | 0.11 (0.10–0.13)
Sildenafil | 50 mg single dose | 75 mg q.d. | 16 | 0.92 (0.85–0.99) | 0.98 (0.92–1.05) | 1.04 (0.98–1.09)
CI=Confidence Interval; N=maximum number of subjects with data; N.A.=not available; ↑=increase; ↓=decrease; ↔=no change; q.d.=once daily; b.i.d.=twice daily

Table 12: Drug Interactions: Pharmacokinetic Parameters for Coadministered Drugs in the Presence of EDURANT
Coadministered Drug | Dose/Schedule |  | N | Mean Ratio of Coadministered Drug Pharmacokinetic Parameters With/Without EDURANT (90% CI); No Effect=1.00
Coadministered Drug | Coadministered Drug | Rilpivirine | N | Cmax | AUC | Cmin
Coadministration With HIV Protease Inhibitors (PIs)
Darunavir/ritonavir | 800/100 mg q.d. | 150 mg q.d. [This interaction study has been performed with a dose higher than the recommended dose for EDURANT (25 mg once daily) assessing the maximal effect on the coadministered drug.] | 15 | 0.90 (0.81–1.00) | 0.89 (0.81–0.99) | 0.89 (0.68–1.16)
Lopinavir/ritonavir (soft gel capsule) | 400/100 mg b.i.d. | 150 mg q.d. | 15 | 0.96 (0.88–1.05) | 0.99 (0.89–1.10) | 0.89 (0.73–1.08)
Coadministration With HIV Nucleoside or Nucleotide Reverse Transcriptase Inhibitors (NRTIs/N[t]RTIs)
Didanosine | 400 mg q.d. delayed release capsules taken 2 hours before rilpivirine | 150 mg q.d. | 13 | 0.96 (0.80–1.14) | 1.12 (0.99–1.27) | N.A.
Tenofovir disoproxil fumarate | 300 mg q.d. | 150 mg q.d. | 16 | 1.19 (1.06–1.34) | 1.23 (1.16–1.31) | 1.24 (1.10–1.38)
Coadministration With HIV Integrase Strand Transfer Inhibitors
Cabotegravir | 30 mg q.d. | 25 mg q.d. | 11 | 1.05 (0.96–1.15) | 1.12 (1.05–1.19) | 1.14 (1.04–1.24)
Raltegravir | 400 mg b.i.d. | 25 mg q.d. | 23 | 1.10 (0.77–1.58) | 1.09 (0.81–1.47) | 1.27 (1.01–1.60)
Coadministration With other Antivirals
Simeprevir | 150 mg q.d. | 25 mg q.d. | 21 | 1.10 (0.97–1.26) | 1.06 (0.94–1.19) | 0.96 (0.83–1.11)
Coadministration With Drugs other than Antiretrovirals
Acetaminophen | 500 mg single dose | 150 mg q.d. | 16 | 0.97 (0.86–1.10) | 0.91 (0.86–0.97) | N.A.
Atorvastatin | 40 mg q.d. | 150 mg q.d. | 16 | 1.35 (1.08–1.68) | 1.04 (0.97–1.12) | 0.85 (0.69–1.03)
2-hydroxy-atorvastatin |  |  | 16 | 1.58 (1.33–1.87) | 1.39 (1.29–1.50) | 1.32 (1.10–1.58)
4-hydroxy-atorvastatin |  |  | 16 | 1.28 (1.15–1.43) | 1.23 (1.13–1.33) | N.A.
Chlorzoxazone | 500 mg single dose taken 2 hours after rilpivirine | 150 mg q.d. | 16 | 0.98 (0.85–1.13) | 1.03 (0.95–1.13) | N.A.
Digoxin | 0.5 mg single dose | 25 mg q.d. | 22 | 1.06 (0.97–1.17) | 0.98 (0.93–1.04) [AUC (0–last)] | N.A.
Ethinylestradiol | 0.035 mg q.d. | 25 mg q.d. | 17 | 1.17 (1.06–1.30) | 1.14 (1.10–1.19) | 1.09 (1.03–1.16)
Norethindrone | 1 mg q.d. |  | 17 | 0.94 (0.83–1.06) | 0.89 (0.84–0.94) | 0.99 (0.90–1.08)
Ketoconazole | 400 mg q.d. | 150 mg q.d. | 14 | 0.85 (0.80–0.90) | 0.76 (0.70–0.82) | 0.34 (0.25–0.46)
R(-) methadone | 60–100 mg q.d., individualized dose | 25 mg q.d. | 13 | 0.86 (0.78–0.95) | 0.84 (0.74–0.95) | 0.78 (0.67–0.91)
S(+) methadone |  |  | 13 | 0.87 (0.78–0.97) | 0.84 (0.74–0.96) | 0.79 (0.67–0.92)
Metformin | 850 mg single dose | 25 mg q.d. | 20 | 1.02 (0.95–1.10) | 0.97 (0.90–1.06) [N (maximum number of subjects with data) for AUC (0–∞)=15] | N.A.
Omeprazole | 20 mg q.d. | 150 mg q.d. | 15 | 0.86 (0.68–1.09) | 0.86 (0.76–0.97) | N.A.
Rifampin | 600 mg q.d. | 150 mg q.d. | 16 | 1.02 (0.93–1.12) | 0.99 (0.92–1.07) | N.A.
25-desacetylrifampin |  |  | 16 | 1.00 (0.87–1.15) | 0.91 (0.77–1.07) | N.A.
Sildenafil | 50 mg single dose | 75 mg q.d. | 16 | 0.93 (0.80–1.08) | 0.97 (0.87–1.08) | N.A.
N-desmethyl-sildenafil |  |  | 16 | 0.90 (0.80–1.02) | 0.92 (0.85–0.99) | N.A.
CI=Confidence Interval; N=maximum number of subjects with data; N.A.=not available; ↑=increase; ↓=decrease; ↔=no change; q.d.=once daily; b.i.d.=twice daily

12.4 Microbiology

Mechanism of Action

Rilpivirine is a diarylpyrimidine non-nucleoside reverse transcriptase inhibitor (NNRTI) of human immunodeficiency virus type 1 (HIV-1) and inhibits HIV-1 replication by non-competitive inhibition of HIV-1 reverse transcriptase (RT). Rilpivirine does not inhibit the human cellular DNA polymerases α, β and γ.

Antiviral Activity in Cell Culture

Rilpivirine exhibited activity against laboratory strains of wild-type HIV-1 in an acutely infected T-cell line with a median EC50value for HIV-1IIIBof 0.73 nM (0.27 ng/mL). Rilpivirine demonstrated limited activity in cell culture against HIV-2 with a median EC50value of 5220 nM (range 2510 to 10830 nM) (920 to 3970 ng/mL).

Rilpivirine demonstrated antiviral activity against a broad panel of HIV-1 group M (subtype A, B, C, D, F, G, H) primary isolates with EC50values ranging from 0.07 to 1.01 nM (0.03 to 0.37 ng/mL) and was less active against group O primary isolates with EC50values ranging from 2.88 to 8.45 nM (1.06 to 3.10 ng/mL).

The antiviral activity of rilpivirine was not antagonistic when combined with the NNRTIs efavirenz, etravirine or nevirapine; the N(t)RTIs abacavir, didanosine, emtricitabine, lamivudine, stavudine, tenofovir or zidovudine; the PIs amprenavir, atazanavir, darunavir, indinavir, lopinavir, nelfinavir, ritonavir, saquinavir or tipranavir; the fusion inhibitor enfuvirtide; the CCR5 co-receptor antagonist maraviroc, or the integrase strand transfer inhibitor raltegravir.

Resistance

In Cell Culture

Rilpivirine-resistant strains were selected in cell culture starting from wild-type HIV-1 of different origins and subtypes as well as NNRTI resistant HIV-1. The frequently observed amino acid substitutions that emerged and conferred decreased phenotypic susceptibility to rilpivirine included: L100I, K101E, V106I and A, V108I, E138K and G, Q, R, V179F and I, Y181C and I, V189I, G190E, H221Y, F227C and M230I and L.

In Treatment-Naïve Adult Subjects

In the Week 96 pooled resistance analysis of the Phase 3 trials TMC278-C209 and TMC278-C215, the emergence of resistance was greater among subjects' viruses in the EDURANT arm compared to the efavirenz arm, and was dependent on baseline viral load. In the pooled resistance analysis, 58% (57/98) of the subjects who qualified for resistance analysis (resistance analysis subjects) in the EDURANT arm had virus with genotypic and/or phenotypic resistance to rilpivirine compared to 45% (25/56) of the resistance analysis subjects in the efavirenz arm who had genotypic and/or phenotypic resistance to efavirenz. Moreover, genotypic and/or phenotypic resistance to a background drug (emtricitabine, lamivudine, tenofovir, abacavir or zidovudine) emerged in viruses from 52% (51/98) of the resistance analysis subjects in the rilpivirine arm compared to 23% (13/56) in the efavirenz arm.

Emerging NNRTI substitutions in the rilpivirine resistance analysis of subjects' viruses included V90I, K101E/P/T, E138K/A/Q/G, V179I/L, Y181C/I, V189I, H221Y, F227C/L and M230L, which were associated with a rilpivirine phenotypic fold change range of 2.6 – 621. The E138K substitution emerged most frequently during rilpivirine treatment commonly in combination with the M184I substitution. The emtricitabine and lamivudine resistance-associated substitutions M184I or V and NRTI resistance-associated substitutions (K65R/N, A62V, D67N/G, K70E, Y115F, T215S/T, or K219E/R) emerged more frequently in rilpivirine resistance analysis subjects compared to efavirenz resistance analysis subjects (see Table 13).

NNRTI- and NRTI-resistance substitutions emerged less frequently in resistance analysis of viruses from subjects with baseline viral load of ≤100,000 copies/mL compared to viruses from subjects with baseline viral load of >100,000 copies/mL: 26% (14/54) compared to 74% (40/54) of NNRTI-resistance substitutions and 22% (11/50) compared to 78% (39/50) of NRTI-resistance substitutions. This difference was also observed for the individual emtricitabine/lamivudine and tenofovir resistance substitutions: 23% (11/47) compared to 77% (36/47) for M184I/V and 0% (0/8) compared to 100% (8/8) for K65R/N. Additionally, NNRTI- and NRTI-resistance substitutions emerged less frequently in the resistance analysis of viruses from subjects with baseline CD4+ cell counts ≥200 cells/mm^3compared to viruses from subjects with baseline CD4+ cell counts <200 cells/mm^3: 37% (20/54) compared to 63% (34/54) of NNRTI-resistance substitutions and 28% (14/50) compared to 72% (36/50) of NRTI-resistance substitutions.

Table 13: Proportion of Resistance Analysis Subjects [Subjects who qualified for resistance analysis.] with Frequently Emerging Reverse Transcriptase Substitutions from the Pooled Phase 3 TMC278-C209 and TMC278-C215 Trials in the Week 96 Analysis
 | TMC278-C209 and TMC278-C215 N=1368
 | EDURANT + BR N=686 | Efavirenz + BR N=682
Subjects who Qualified for Resistance Analysis | 15% (98/652) | 9% (56/604)
Subjects with Evaluable Post-Baseline Resistance Data | 87 | 43
Emerging NNRTI Substitutions [V90, L100, K101, K103, V106, V108, E138, V179, Y181, Y188, V189, G190, H221, P225, F227 or M230]
Any | 62% (54/87) | 53% (23/43)
V90I | 13% (11/87) | 2% (1/43)
K101E/P/T/Q | 20% (17/87) | 9% (4/43)
K103N | 1% (1/87) | 40% (17/43)
E138K/A/Q/G | 40% (35/87) | 2% (1/43)
E138K+ M184I [This combination of NNRTI and NRTI substitutions is a subset of those with the E138K.] | 25% (22/87) | 0
V179I/L/D | 6% (5/87) | 7% (3/43)
Y181C/I/S | 10% (9/87) | 2% (1/43)
V189I | 8% (7/87) | 2% (1/43)
H221Y | 9% (8/87) | 0
Emerging NRTI Substitutions [A62V, K65R/N, D67N/G, K70E, L74I, V75I, Y115F, M184I/V, L210F, T215S/T, K219E/R]
Any | 57% (50/87) | 30% (13/43)
M184I/V | 54% (47/87) | 26% (11/43)
K65R/N | 9% (8/87) | 5% (2/43)
A62V, D67N/G, K70E, Y115F, T215S/T or K219E/R [These substitutions emerged in addition to the primary substitutions M184V/I or K65R/N; A62V (n=3), D67N/G (n=3), K70E (n=4), Y115F (n=2), T215S/T (n=1), K219E/R (n=8) in rilpivirine resistance analysis subjects.] | 21% (18/87) | 2% (1/43)
BR=background regimen

Treatment--Naïve HIV-1-Infected Pediatric Subjects

In trial TMC278-C213 Cohort 1, a single-arm, open-label Phase 2 trial in antiretroviral treatment-naïve HIV-1-infected pediatric subjects ≥12 to less than 18 years [see Clinical Studies (14.3)] , rilpivirine resistance-associated substitutions were observed in 62.5% (5/8) of subjects with virologic failure and post-baseline genotypic data at 48 weeks with 4 of 5 having ≥2.5-fold decrease in susceptibility to rilpivirine. In addition, 4 of the 5 subjects with rilpivirine resistance substitutions also had at least 1 treatment-emergent resistance substitution to nucleos(t)ide reverse transcriptase inhibitors.

In trial TMC278-C213 Cohort 2, a single-arm, open-label Phase 2 trial in antiretroviral treatment-naïve HIV-1-infected pediatric subjects 6 to less than 12 years of age [see Clinical Studies (14.4)] , 83% (5/6) of subjects with virologic failure (3 subjects failed ≤48 weeks and 3 subjects failed after 48 weeks) had treatment-emergent rilpivirine resistance-associated substitutions with 4 showing reduced rilpivirine susceptibility. Additionally, 4 of the virologic failures also had treatment-emergent resistance substitutions to nucleos(t)ide reverse transcriptase inhibitors.

The emergent rilpivirine resistance-associated substitutions in pediatric patients are consistent with those seen in adults failing on a rilpivirine-containing regimen (see Table 13).

Cross-Resistance

Site-Directed NNRTI Mutant Virus

Cross-resistance has been observed among NNRTIs. The single NNRTI substitutions K101P, Y181I and Y181V conferred 52-fold, 15-fold and 12-fold decreased susceptibility to rilpivirine, respectively. The combination of E138K and M184I showed 6.7-fold reduced susceptibility to rilpivirine compared to 2.8-fold for E138K alone. The K103N substitution did not result in reduced susceptibility to rilpivirine by itself. However, the combination of K103N and L100I resulted in a 7-fold reduced susceptibility to rilpivirine. Combinations of 2 or 3 NNRTI resistance-associated substitutions had decreased susceptibility to rilpivirine (fold change range of 3.7 – 554) in 38% and 66% of mutants analyzed, respectively.

Treatment-Naïve HIV-1-Infected Adult Subjects

Considering all available cell culture and clinical data, any of the following amino acid substitutions, when present at baseline, are likely to decrease the antiviral activity of rilpivirine: K101E, K101P, E138A, E138G, E138K, E138R, E138Q, V179L, Y181C, Y181I, Y181V, Y188L, H221Y, F227C, M230I or M230L.

Cross-resistance to efavirenz, etravirine and/or nevirapine is likely after virologic failure and development of rilpivirine resistance. In the Week 96 pooled analyses of the Phase 3 TMC278-C209 and TMC278-C215 clinical trials, 50 of the 87 (57%) rilpivirine resistance analysis subjects with post-baseline resistance data had virus with decreased susceptibility to rilpivirine (≥2.5-fold change). Of these, 86% (n=43/50) were resistant to efavirenz (≥3.3-fold change), 90% (n=45/50) were resistant to etravirine (≥3.2-fold change) and 62% (n=31/50) were resistant to nevirapine (≥6-fold change). In the efavirenz arm, 3 of the 21 (14%) efavirenz resistance analysis subjects' viruses were resistant to etravirine and rilpivirine, and 95% (n=20/21) were resistant to nevirapine. Virus from subjects experiencing virologic failure on EDURANT developed more NNRTI resistance-associated substitutions conferring more cross-resistance to the NNRTI class and had a higher likelihood of cross-resistance to all NNRTIs in the class compared to virus from subjects who failed on efavirenz.

13 NONCLINICAL TOXICOLOGY

13.1 Carcinogenesis, Mutagenesis, Impairment of Fertility

Carcinogenesis and Mutagenesis

Two-year carcinogenicity studies in mice and rats were conducted with rilpivirine. In rats, there were no drug related neoplasms at exposures 3 times those observed in humans (12 years of age and older and weighing greater than 32 kg) and ≥1.4 times relative to the predicted exposures in children (2 to less than 12 years of age, weighing at least 14 kg) at the recommended daily dose. In mice, rilpivirine was positive for hepatocellular neoplasms in both males and females. The observed hepatocellular findings in mice may be rodent-specific. At the lowest tested dose in the mouse carcinogenicity study, the systemic exposure to rilpivirine was 21 times that observed in humans (12 years of age and older and weighing greater than 32 kg) and ≥12 times relative to the predicted exposures in children (2 to less than 12 years of age, weighing at least 14 kg) at the recommended daily dose.

Rilpivirine was not genotoxic in the bacterial reverse mutation assay, mouse lymphoma assay, or in the in vivorodent micronucleus assay.

Impairment of Fertility

In rat fertility and early embryonic development studies with rilpivirine, no effects on fertility were observed at rilpivirine exposures (AUC) greater than 36 times (male) and 40 times (female) the exposure in humans (12 years of age and older and weighing at least 32 kg) at the recommended daily dose of 25 mg.

14 CLINICAL STUDIES

14.1 Treatment-Naïve Adult Subjects

The evidence of efficacy of EDURANT is based on the analyses of 48- and 96-week data from 2 randomized, double-blinded, active controlled, Phase 3 trials TMC278-C209 (ECHO) and TMC278-C215 (THRIVE) in antiretroviral treatment-naïve adults. Antiretroviral treatment-naïve HIV-1 infected subjects enrolled in the Phase 3 trials had a plasma HIV-1 RNA ≥5000 copies/mL and were screened for susceptibility to N(t)RTIs and for absence of specific NNRTI resistance-associated substitutions (RASs). The Phase 3 trials were identical in design, apart from the background regimen (BR). In TMC278-C209, the BR was fixed to the N(t)RTIs, tenofovir disoproxil fumarate plus emtricitabine. In TMC278-C215, the BR consisted of 2 investigator-selected N(t)RTIs: tenofovir disoproxil fumarate plus emtricitabine or zidovudine plus lamivudine or abacavir plus lamivudine. In both trials, randomization was stratified by screening viral load. In TMC278-C215, randomization was also stratified by N(t)RTI BR.

In the pooled analysis for TMC278-C209 and TMC278-C215, demographics and baseline characteristics were balanced between the EDURANT arm and the efavirenz arm. Table 14 displays selected demographic and baseline disease characteristics of the subjects in the EDURANT and efavirenz arms.

Table 14: Demographic and Baseline Disease Characteristics of Antiretroviral Treatment-Naïve HIV-1-Infected Adult Subjects in the TMC278-C209 and TMC278-C215 Trials (Pooled Analysis)
 | Pooled Data from the Phase 3 TMC278-C209 and TMC278-C215 Trials
 | EDURANT + BR N=686 | Efavirenz + BR N=682
Demographic Characteristics
Median Age, years (range) | 36 (18–78) | 36 (19–69)
Sex
Male | 76% | 76%
Female | 24% | 24%
Race
White | 61% | 60%
Black/African American | 24% | 23%
Asian | 11% | 14%
Other | 2% | 2%
Not allowed to ask per local regulations | 1% | 1%
Baseline Disease Characteristics
Median Baseline Plasma HIV-1 RNA (range), log10copies/mL | 5.0 (2–7) | 5.0 (3–7)
Percentage of Patients with Baseline Plasma Viral Load:
≤100,000 | 54% | 48%
>100,000 to ≤500,000 | 36% | 40%
>500,000 | 10% | 12%
Median Baseline CD4+ Cell Count (range), cells/mm^3 | 249 (1–888) | 260 (1–1137)
Percentage of Subjects with:
Hepatitis B/C Virus Co-infection | 7% | 10%
Percentage of Patients with the Following Background Regimens:
tenofovir disoproxil fumarate plus emtricitabine | 80% | 80%
zidovudine plus lamivudine | 15% | 15%
abacavir plus lamivudine | 5% | 5%
BR=background regimen

Week 96 efficacy outcomes for subjects treated with EDURANT 25 mg once daily from the pooled analysis are shown in Table 15. The incidence of virologic failure was higher in the EDURANT arm than the efavirenz arm at Week 96. Virologic failures and discontinuations due to adverse events mostly occurred in the first 48 weeks of treatment. Regardless of HIV-1 RNA at the start of therapy, more EDURANT treated subjects with CD4+ cell count less than 200 cells/mm^3 experienced virologic failure compared to EDURANT treated subjects with CD4+ cell count greater than or equal to 200 cells/mm^3.

Table 15: Virologic Outcome of Randomized Treatment of Studies TMC278-C209 and TMC278-C215 (Pooled Data) at Week 96
 | EDURANT + BR N=686 | Efavirenz + BR N=682
HIV-1 RNA <50 copies/mL [CI=Predicted difference (95% CI) of response rate is -0.2 (-4.7; 4.3) at Week 96.] | 76% | 77%
HIV-1 RNA ≥50 copies/mL [Includes subjects who had ≥50 copies/mL in the Week 96 window, subjects who discontinued early due to lack or loss of efficacy, subjects who discontinued for reasons other than an adverse event, death or lack or loss of efficacy and at the time of discontinuation had a viral value of ≥50 copies/mL, and subjects who had a switch in background regimen that was not permitted by the protocol.] | 16% | 10%
No virologic data at Week 96 window Reasons
Discontinued study due to adverse event or death [Includes subjects who discontinued due to an adverse event or death if this resulted in no on-treatment virologic data in the Week 96 window.] | 4% | 8%
Discontinued study for other reasons and last available HIV-1 RNA <50 copies/mL (or missing) [Includes subjects who discontinued for reasons other than an adverse event, death or lack or loss of efficacy, e.g., withdrew consent, loss to follow-up, etc.] | 4% | 5%
Missing data during window but on study | <1% | <1%
HIV-1 RNA <50 copies/mL by Baseline HIV-1 RNA (copies/mL)
≤100,000 | 82% | 78%
>100,000 | 70% | 75%
HIV-1 RNA ≥50 copies/mL by Baseline HIV-1 RNA (copies/mL)
≤100,000 | 9% | 8%
>100,000 | 24% | 11%
HIV-1 RNA <50 copies/mL by CD4+ cell count (cells/mm^3)
<200 | 68% | 74%
≥200 | 81% | 77%
HIV-1 RNA ≥50 copies/mL by CD4+ cell count (cells/mm^3)
<200 | 27% | 10%
≥200 | 10% | 9%
N=total number of subjects per treatment group; BR=background regimen.
Note: Analysis was based on the last observed viral load data within the Week 96 window (Week 90–103), respectively.

At Week 96, the mean CD4+ cell count increase from baseline was 228 cells/mm^3 for EDURANT-treated subjects and 219 cells/mm^3 for efavirenz-treated subjects in the pooled analysis of the TMC278-C209 and TMC278-C215 trials.

Study TMC278-C204 was a randomized, active-controlled, Phase 2b trial in antiretroviral treatment-naïve HIV-1-infected adult subjects consisting of 2 parts: an initial 96 weeks, partially-blinded dose-finding part [EDURANT doses blinded] followed by a long-term, open-label part. After Week 96, subjects randomized to one of the 3 doses of EDURANT were switched to EDURANT 25 mg once daily. Subjects in the control arm received efavirenz 600 mg once daily in addition to a BR in both parts of the study. The BR consisted of 2 investigator-selected N(t)RTIs: zidovudine plus lamivudine or tenofovir disoproxil fumarate plus emtricitabine.

Study TMC278-C204 enrolled 368 HIV-1-infected treatment-naïve adult subjects who had a plasma HIV-1 RNA ≥5000 copies/mL, previously received ≤2 weeks of treatment with an N(t)RTI or protease inhibitor, had no prior use of NNRTIs, and were screened for susceptibility to N(t)RTI and for absence of specific NNRTI RASs.

At 96 weeks, the proportion of subjects with <50 HIV-1 RNA copies/mL receiving EDURANT 25 mg (N=93) compared to subjects receiving efavirenz (N=89) was 76% and 71%, respectively. The mean increase from baseline in CD4+ counts was 146 cells/mm^3in subjects receiving EDURANT 25 mg and 160 cells/mm^3in subjects receiving efavirenz.

At 240 weeks, 60% (56/93) of subjects who originally received 25 mg once daily achieved HIV RNA <50 copies/mL compared to 57% (51/89) of subjects in the control group.

14.2 Virologically-Suppressed Adults Treated in Combination with Cabotegravir

The use of EDURANT in combination with VOCABRIA (cabotegravir) as an oral lead-in and in patients who miss planned injections with CABENUVA (cabotegravir extended-release injectable suspension; rilpivirine extended-release injectable suspension) was evaluated in two Phase 3 randomized, multicenter, active-controlled, parallel-arm, open-label, non-inferiority trials (Trial 201584: FLAIR [NCT02938520], Trial 201585: ATLAS [NCT2951052]), and one Phase 3b randomized, multicenter, parallel-group, open-label, non-inferiority trial (Trial 207966: ATLAS-2M [NCT03299049]) in subjects who were virologically suppressed (HIV-1 RNA <50 copies/mL). See full prescribing information for VOCABRIA and CABENUVA for additional information.

14.3 Treatment-Naïve Pediatric Subjects (≥12 to less than 18 Years of Age)

The pharmacokinetics, safety, tolerability and efficacy of EDURANT 25 mg once daily, in combination with an investigator-selected background regimen (BR) containing two NRTIs, was evaluated in trial TMC278-C213 Cohort 1, a single-arm, open-label Phase 2 trial in antiretroviral treatment-naïve HIV-1 infected pediatric subjects 12 to less than 18 years of age and weighing at least 32 kg. Thirty six (36) subjects were enrolled in the trial to complete at least 48 weeks of treatment. The 36 subjects had a median age of 14.5 years (range: 12 to 17 years), and were 56% female, 89% Black and 11% Asian.

In the efficacy analysis, most subjects (75%; 28/36) had baseline HIV RNA <100,000 copies/mL. For these 28 subjects the median baseline plasma HIV-1 RNA was 44,250 (range: 2,060–92,600 copies/mL) and the median baseline CD4+ cell count was 445.5 cells/mm^3(range: 123 to 983 cells/mm^3).

Among the subjects who had baseline HIV RNA ≤100,000, the proportion with HIV-1 RNA <50 copies/mL at Week 48 was 79% (22/28), versus 50% (4/8) in those with >100,000 copies/mL. The proportion of virologic failures among subjects with a baseline viral load ≤100,000 copies/mL was 21% (6/28), versus 38% (3/8) in those with >100,000 copies/mL. At Week 48, the mean increase in CD4+ cell count from baseline was 201.2 cells/mm^3.

14.4 Treatment-Naïve Pediatric Subjects (2 to less than 12 Years of Age)

The pharmacokinetics, safety, tolerability and efficacy of EDURANT and EDURANT PED weight-adjusted doses 25, 15 and 12.5 mg once daily in combination with an investigator-selected BR containing two NRTIs, was evaluated in trial TMC278-C213 Cohort 2, a single-arm, open-label Phase 2 trial in antiretroviral treatment-naïve HIV-1 infected pediatric subjects 6 to less than 12 years of age and weighing at least 17 kg. The Week 48 analysis included 18 subjects, 17 (94%) subjects completed the 48-week treatment period, and 1 (6%) subject discontinued the study early due to reaching a virologic endpoint. The 18 subjects had a median age of 9 years (range 6 to 11 years) and the median weight at baseline was 25 kg (range 17 to 51 kg). 89% were Black and 39% were female. The median baseline plasma viral load was 55,400 (range 567–149,000) copies/mL, and the median absolute baseline CD4+ cell count was 432.5 (range 12–2,068) cells/µL.

The number of subjects with HIV-1 RNA <50 copies/mL at Week 48 was 13/18 (72%), while 3/18 (17%) subjects had HIV-1 RNA ≥50 copies/mL at Week 48 [see Microbiology (12.4)] . Two out of 18 (11%) participants in the 15 mg once daily (20 to ≤25 kg) dose-weight group had missing viral load data at Week 48 but remained on study. The viral load for these 2 subjects was <50 copies/mL, post-Week 48. The mean increase (SE) in CD4+ from baseline was 215.9 (62.42) cells/µL at Week 48.

The safety and efficacy of EDURANT and EDURANT PED in treatment naïve pediatric subjects 2 to less than 6 years of age is supported by evidence from adequate and well-controlled studies of EDURANT in adults with additional population pharmacokinetic data from adults and pediatric subjects 6 years and older [see Use in Specific Populations (8.4)and Clinical Pharmacology (12.3)] .

16 HOW SUPPLIED/STORAGE AND HANDLING

STORAGE AND HANDLING

EDURANT Tablets

EDURANT® (rilpivirine) 25 mg tablets are supplied as white to off-white, film-coated, round, biconvex, 6.4 mm tablets. Each tablet contains 27.5 mg of rilpivirine hydrochloride, which is equivalent to 25 mg of rilpivirine. Each tablet is debossed with "TMC" on one side and "25" on the other side.

EDURANT 25 mg tablets are packaged in bottles in the following configuration: 25 mg tablets-bottles of 30 (NDC 59676-278-01).

Store EDURANT tablets in the original bottle in order to protect from light. Store EDURANT tablets at 20° to 25°C (68° to 77°F); with excursions permitted to 15° to 30°C (59° to 86°F) [see USP controlled room temperature].

STORAGE AND HANDLING

EDURANT PED Tablets for Oral Suspension

EDURANT® PED (rilpivirine) 2.5 mg tablets for oral suspension are supplied as white to almost white, round 6.5 mm tablets, debossed with "TMC" on one side and "PED" on the other side. Each tablet for oral suspension contains 2.75 mg rilpivirine hydrochloride equivalent to 2.5 mg rilpivirine.

EDURANT PED 2.5 mg tablets for oral suspension are packaged in aluminum cold form film blister with integrated desiccant and an aluminum peelable lidding foil. Each blister contains 10 tablets with 9 blisters per carton (NDC 59676-280-90).

Store EDURANT PED tablets for oral suspension in the original package in order to protect from light and moisture. Store at 20° to 25°C (68° to 77°F); with excursions permitted to 15° to 30°C (59° to 86°F) [see USP controlled room temperature].

17 PATIENT COUNSELING INFORMATION

Advise the patient to read the FDA-approved patient labeling (Patient Information and Instructions for Use).

Severe Skin and Hypersensitivity Reactions

Advise patients to immediately contact their healthcare provider if they develop a rash. Instruct patients to immediately stop taking EDURANT or EDURANT PED and seek medical attention if they develop a rash associated with any of the following symptoms as it may be a sign of more serious reactions such as DRESS severe hypersensitivity: fever, blisters, mucosal involvement, eye inflammation (conjunctivitis), severe allergic reaction causing a swelling of the face, eyes, lips, mouth, tongue or throat, which may lead to difficulty swallowing or breathing, and any signs and symptoms of liver problems as it may be a sign of a more serious reaction. Advise patients that if severe rash occurs, they will be closely monitored, laboratory tests will be performed and appropriate therapy will be initiated [see Warnings and Precautions (5.1)] .

Hepatotoxicity

Inform patients that hepatotoxicity has been reported with EDURANT. Inform patients that laboratory monitoring for hepatotoxicity during therapy with EDURANT or EDURANT PED is recommended, especially for patients with underlying liver disease such as hepatitis B or C virus infection [see Warnings and Precautions (5.2)].

Depressive Disorders

Inform patients that depressive disorders (depressed mood, depression, dysphoria, major depression, mood altered, negative thoughts, suicide attempt, suicidal ideation) have been reported with EDURANT. Advise patients to seek immediate medical evaluation if they experience depressive symptoms [see Warnings and Precautions (5.3)] .

Drug Interactions

EDURANT or EDURANT PED may interact with many drugs; therefore, advise patients to report to their healthcare provider the use of any other prescription or nonprescription medication or herbal products, including St. John's wort [see Contraindications (4), Warnings and Precautions (5.4), and Drug Interactions (7)] .

For patients concomitantly receiving rifabutin, the EDURANT dose should be increased to 50 mg once daily, taken with a meal. When rifabutin coadministration is stopped, the EDURANT dose should be decreased to 25 mg once daily, taken with a meal [see Dosage and Administration (2.7)] .

Immune Reconstitution Syndrome

Advise patients to inform their healthcare provider immediately of any signs or symptoms of infection as inflammation from previous infection may occur soon after combination antiretroviral therapy, including when EDURANT or EDURANT PED is started [see Warnings and Precautions (5.5)].

EDURANT Tablets and EDURANT PED Tablets for Oral Suspension Are Not Substitutable

Advise patients that EDURANT and EDURANT PED have differing pharmacokinetic profiles and are not substitutable on a milligram-per-milligram basis. Advise patients or their care providers that patients switching from EDURANT PED tablets for oral suspension to EDURANT tablets must adjust the dose [see Dosage and Administration (2.1, 2.3)and Warnings and Precautions (5.6)].

To avoid a dosing error from using the wrong formulation of EDURANT, strongly advise patients and caregivers to visually inspect the tablets to verify the correct formulation each time the prescription is filled [see Dosage and Administration (2), Warnings and Precautions (5.6), and How Supplied/Storage and Handling (16)].

Administration Instructions

Advise patients to take EDURANT or EDURANT PED with a meal once a day as prescribed. A protein drink or yogurt alone does not replace a meal [see Clinical Pharmacology (12.3)] . EDURANT and EDURANT PED must always be used in combination with other antiretroviral drugs. Advise patients not to alter the dose of EDURANT or EDURANT PED or discontinue therapy without consulting their physician.

Inform patients and caregivers that EDURANT PED tablets for oral suspension should be dispersed in drinking water and should not be crushed, chewed, or swallowed whole [see Dosage and Administration (2.4)].

If the patient misses a dose of EDURANT or EDURANT PED within 12 hours of the time it is usually taken, advise the patient to take EDURANT or EDURANT PED with a meal as soon as possible and then take the next dose of EDURANT or EDURANT PED at the regularly scheduled time. If a patient misses a dose of EDURANT or EDURANT PED by more than 12 hours, advise the patient to not take the missed dose, but resume the usual dosing schedule. Inform the patient that he or she should not take more or less than the prescribed dose of EDURANT or EDURANT PED at any one time.

Pregnancy Registry

Advise patients that there is a pregnancy exposure registry that monitors pregnancy outcomes in women exposed to EDURANT during pregnancy [see Use in Specific Populations (8.1)].

Lactation

Inform individuals with HIV-1 infection that the potential risks of breastfeeding include: (1) HIV-1 transmission (in HIV-1-negative infants), (2) developing viral resistance (in HIV-1-positive infants), and (3) adverse reactions in a breastfed infant similar to those seen in adults [see Use in Specific Populations (8.2)] .

Manufactured for:
Janssen Products, LP
Horsham, PA 19044, USA

For patent information: www.janssenpatents.com

© Johnson & Johnson and its affiliates 2011, 2024

PATIENT INFORMATION

EDURANT® (ee dur ant)
(rilpivirine)
tablets, for oral use

EDURANT® PED (ee dur ant ped)
(rilpivirine)
tablets, for oral suspension

What are EDURANT and EDURANT PED?

- EDURANT and EDURANT PED are prescription medicines that are used with other human immunodeficiency virus-1 (HIV-1) medicines to treat HIV-1 infection in people 2 years of age and older and who weigh at least 31 pounds (lbs) or 14 kilograms (kg) who:
  - have never taken HIV-1 medicines before, and
  - have an amount of HIV-1 in their blood (this is called 'viral load') that is no more than 100,000 copies/mL.
- EDURANT is also used with oral VOCABRIA (cabotegravir) for short term treatment of HIV-1 infection in people 12 years of age and older and who weigh at least 77 lbs (35 kg) when their healthcare provider determines that they meet certain requirements.

HIV-1 is the virus that causes AIDS (Acquired Immune Deficiency Syndrome).
If you take EDURANT in combination with oral VOCABRIA (cabotegravir), you should also read the Patient Information that comes with oral VOCABRIA (cabotegravir).
It is not known if EDURANT or EDURANT PED is safe and effective in children less than 2 years of age or who weigh less than 31 Ibs (14 kg).

Do not take EDURANT or EDURANT PED if you are taking any of the following medicines:

- carbamazepine
- phenobarbital
- rifampin
- dexamethasone (more than a single dose treatment)
- esomeprazole
- omeprazole
- rabeprazole

- oxcarbazepine
- phenytoin
- rifapentine
- St. John's wort (Hypericum perforatum)
- lansoprazole
- pantoprazole

Before taking EDURANT or EDURANT PED, tell your healthcare provider about all your medical conditions, including if you:

- have ever had a severe skin rash or an allergic reaction to medicines that contain rilpivirine
- have or had liver problems, including hepatitis B or C virus infection
- have kidney problems
- have ever had a mental health problem
- are pregnant or plan to become pregnant. It is not known if EDURANT or EDURANT PED will harm your unborn baby. Tell your healthcare provider if you become pregnant during treatment with EDURANT or EDURANT PED.
  - Pregnancy Registry: There is a pregnancy registry for women who take EDURANT during pregnancy. The purpose of this registry is to collect information about the health of you and your baby. Talk with your healthcare provider about how you can take part in this registry.
- are breastfeeding or plan to breastfeed. EDURANT or EDURANT PED can pass into your breast milk. Talk with your healthcare provider about the following risks of breastfeeding during treatment with EDURANT or EDURANT PED:
  - The HIV-1 virus may pass to your baby if your baby does not have the HIV-1 infection.
  - The HIV-1 virus may become harder to treat if your baby has HIV-1 infection.
  - Your baby may get side effects from EDURANT or EDURANT PED.

Tell your healthcare provider about all the medicines you take, including prescription and over-the-counter medicines, vitamins, and herbal supplements. Some medicines interact with EDURANT or EDURANT PED. Keep a list of your medicines to show your healthcare provider and pharmacist when you get a new medicine.

- You can ask your healthcare provider or pharmacist for a list of medicines that interact with EDURANT or EDURANT PED.
- Do not start taking a new medicine without telling your healthcare provider. Your healthcare provider can tell you if it is safe to take EDURANT or EDURANT PED with other medicines.

How should I take EDURANT or EDURANT PED?
See the " Instructions for Use" for detailed instructions on how to prepare and give a dose of EDURANT PED tablets for oral suspension.

- Take EDURANT or EDURANT PED exactly as your healthcare provider tells you to.
- Take EDURANT or EDURANT PED 1 time each day with a meal. A protein drink or yogurt alone does not replace a meal.
- EDURANT and EDURANT PED must be used with other HIV-1 medicines.
- Do not change your dose or stop taking EDURANT or EDURANT PED without first talking with your healthcare provider.
- Stay under the care of your healthcare provider during treatment with EDURANT or EDURANT PED.
- EDURANT PED tablets for oral suspension provided in a blister package are not the same as EDURANT tablets provided in a bottle and cannot be substituted for each other. Contact your pharmacist or healthcare provider if you did not receive the correct dosage form. Your child's healthcare provider will prescribe EDURANT or EDURANT PED based on your child's weight.
- EDURANT PED tablets for oral suspension must be dispersed in drinking water. Do notcrush, chew, or swallow whole EDURANT PED tablets for oral suspension.
- If you take an H2-receptor antagonist (such as famotidine, cimetidine, nizatidine, or ranitidine), you should take these medicines at least 12 hours before or at least 4 hours after you take EDURANT or EDURANT PED.
- If you take antacids, or other products that contain aluminum, calcium carbonate, or magnesium hydroxide, you should take these medicines at least 2 hours before or at least 4 hours after you take EDURANT or EDURANT PED.
- Do not miss a dose of EDURANT or EDURANT PED.
- If you miss a dose of EDURANT or EDURANT PED within 12 hours of the time you usually take it, take your dose of EDURANT or EDURANT PED with a meal as soon as possible. Then, take your next dose of EDURANT or EDURANT PED at the regularly scheduled time. If you miss a dose of EDURANT or EDURANT PED by more than 12 hours of the time you usually take it, wait and then take the next dose of EDURANT or EDURANT PED at the regularly scheduled time.
- Do not take more than your prescribed dose to make up for a missed dose or take less than your prescribed dose.
- If you take too much EDURANT or EDURANT PED, call your healthcare provider or go to the nearest hospital emergency room right away.
- When your supply of EDURANT or EDURANT PED starts to run low, get more from your healthcare provider or pharmacy. It is important not to run out of EDURANT or EDURANT PED. The amount of HIV in your blood may increase if the medicine is stopped even for a short time.
- When your healthcare provider prescribes use of EDURANT with oral VOCABRIA (cabotegravir):
  - Take EDURANT and oral VOCABRIA (cabotegravir) 1 time a day at about the same time each day with a meal.
  - You will receive treatment with EDURANT tablets in combination with VOCABRIA tablets for one month (at least 28 days) before you receive the long-acting medicine called CABENUVA (cabotegravir; rilpivirine extended-release injectable suspensions) for the first time. This will allow your healthcare provider to assess how well you tolerate these medicines.
  - Your final dose of EDURANT and VOCABRIA tablets should be taken on the same day you receive your first CABENUVA injections.
  - If you miss or plan to miss a scheduled monthly or every 2 months injection of CABENUVA by more than 7 days, call your healthcare provider right away to discuss your treatment options.

What are the possible side effects of EDURANT and EDURANT PED?
EDURANT and EDURANT PED can cause serious side effects including:

- Severe skin rash and allergic reactions. Call your healthcare provider right away if you develop a rash with EDURANT or EDURANT PED. In some cases, rash and allergic reaction may need to be treated in a hospital.
  Stop taking EDURANT or EDURANT PED and get medical help right away if you develop a rash with any of the following signs or symptoms:

- fever
- tiredness
- difficulty breathing or swallowing
- skin blisters
- swelling of the face, lips, mouth, tongue, or throat

- generally ill feeling
- muscle or joint aches
- blisters or mouth sores
- redness or swelling of the eyes (conjunctivitis)

- Liver problems. People with a history of hepatitis B or C virus infection or who have certain liver function test changes may have an increased risk of developing new or worsening changes in certain liver tests during treatment with EDURANT or EDURANT PED. Liver problems have also happened in people without a history of problems or other risk factors. Your healthcare provider may need to do tests to check your liver function before and during treatment with EDURANT or EDURANT PED. Call your healthcare provider right away if you develop any of the following signs or symptoms of liver problems:

- your skin or the white part of your eyes turns yellow (jaundice)
- light colored stools (bowel movements)
- pain, aching, or tenderness on the right side of the stomach area

- loss of appetite
- dark or "tea colored" urine
- nausea or vomiting

- Depression or mood changes. Call your healthcare provider right away if you have any of the following symptoms:
  - feeling sad or hopeless
  - feeling anxious or restless
  - have thoughts of hurting yourself (suicide) or have tried to hurt yourself
- Changes in your immune system (Immune Reconstitution Syndrome) can happen when you start taking HIV medicines. Your immune system may get stronger and begin to fight infections that have been hidden in your body for a long time. Tell your healthcare provider right away if you start having any new symptoms after starting your HIV-1 medicine.

The most common side effects of EDURANT or EDURANT PED include depression, headache, trouble sleeping (insomnia) and rash.
These are not all the possible side effects of EDURANT or EDURANT PED.
Call your doctor for medical advice about side effects. You may report side effects to FDA at 1-800-FDA-1088.

How should I store EDURANT or EDURANT PED?

- Store EDURANT or EDURANT PED at room temperature between 68°F to 77°F (20°C to 25°C).
- Keep EDURANT tablets in the original bottle to protect from light.
- Keep EDURANT PED tablets in the original package to protect from light and moisture.

Keep EDURANT or EDURANT PED and all medicines out of the reach of children.

General information about the safe and effective use of EDURANT and EDURANT PED.
Medicines are sometimes prescribed for purposes other than those listed in a Patient Information leaflet. Do not use EDURANT or EDURANT PED for a condition for which it was not prescribed. Do not give EDURANT or EDURANT PED to other people even if they have the same condition you have. It may harm them.
You can ask your healthcare provider or pharmacist for information about EDURANT or EDURANT PED that is written for health professionals.

What are the ingredients in EDURANT and EDURANT PED?
Active ingredient: rilpivirine.
Inactive ingredients:
EDURANT 25 mg tablets: croscarmellose sodium, lactose monohydrate, magnesium stearate, polysorbate 20, povidone K30 and silicified microcrystalline cellulose. The tablet coating contains hypromellose 2910 6 mPa.s, lactose monohydrate, PEG 3000, titanium dioxide and triacetin.
EDURANT PED 2.5 mg tablets for oral suspension: croscarmellose sodium, lactose monohydrate, mannitol, microcrystalline cellulose, povidone K30, polysorbate 20, sodium lauryl sulfate and sodium stearyl fumarate.
Manufactured for: Janssen Products, LP, Horsham PA 19044, USA
For patent information: www.janssenpatents.com
© Johnson & Johnson and its affiliates 2011, 2024
For more information go to www.EDURANT.com or call 1-800-526-7736

This Patient Information has been approved by the U.S. Food and Drug Administration.

Revised: 11/2024

INSTRUCTIONS FOR USE
EDURANT® PED (ee dur ant ped)
(rilpivirine)
tablets, for oral suspension

This Instructions for Use contains information on how to prepare and give EDURANT PED. Read this Instructions for Use before your child starts taking EDURANT PED for the first time and each time you get a refill. There may be new information. This information does not take the place of talking to your healthcare provider about your child's medical condition or treatment.
Important information you need to know before giving EDURANT PED:

- Take EDURANT PED exactly as your healthcare provider tells you.
- EDURANT PED tablets for oral suspension are provided in a blister package. Each time you receive your child's prescription, check to make sure that you received EDURANT PED tablets.
- EDURANT PED tablets for oral suspension provided in a blister package are not the same as EDURANT tablets provided in a bottle and cannot be substituted for each other. Contact your pharmacist or healthcare provider if you did not receive the correct dosage form.
- Your child's healthcare provider will tell you how many EDURANT PED tablets you will need for your child's dose based on their weight.
- Take EDURANT PED 1 time each day. EDURANT PED tablets must be dispersed in drinking water and must be taken with a meal.
- Do not crush, chew or swallow whole EDURANT PED tablets.

Supplies needed to prepare and give EDURANT PED:

- EDURANT PED tablets

(not included with EDURANT PED):

- a small clean empty cup
- a teaspoon
- room temperature drinking water

Step 1: Prepare EDURANT PED

- Count the number of tablets you need for the prescribed dose and tear each unit from the blister pack along the dotted line.
- For each unit, peel back the foil gently in the direction of the arrow to remove the tablet.
- Do not push the tablets out of the foil as they may break.

Step 2: Place the tablets in a small cup

- Gently place the tablets in a small cup. Do not crush the tablets.
- Add 5 mL (1 teaspoon) of room temperature drinking water to the cup.
- Swirl the cup carefully for 1 to 2 minutes to disperse the tablets. The mixture will start to look cloudy.

If you spill any medicine, clean up the spill. Throw away the rest of the prepared medicine and make a new dose.
You must give the prepared medicine right away. If you do not give the prepared medicine right away, throw away the mixture and prepare a new dose of medicine.

Step 3: Give EDURANT PED

- Give all the prepared medicine right away or add another 5 mL (1 teaspoon) of drinking water, milk, orange juice or applesauce to help take the medicine. Swirl the mixture and give all of the medicine right away. A spoon can be used to give the prepared medicine if needed.
- Make sure the entire dose is taken and no medicine is left in the cup. If there is medicine left in the cup, add another 5 mL (1 teaspoon) of drinking water, milk, orange juice or applesauce. Swirl and give all of the prepared medicine right away.

Step 4: Clean the dosing items

- Wash the cup and teaspoon thoroughly with water and make sure they are clean and dry before preparing the next daily dose.

How should I store EDURANT PED?

- Store EDURANT PED at room temperature between 68°F to 77°F (20°C to 25°C).
- Keep EDURANT PED tablets in the original package to protect from light and moisture.

Keep EDURANT PED and all medicines out of the reach of children.

Manufactured for: Janssen Products, LP, Horsham PA 19044, USA
For patent information: www.janssenpatents.com
© Johnson & Johnson and its affiliates 2011, 2024
For more information go to www.EDURANT.com or call 1-800-526-7736

This Instructions for Use has been approved by the U.S. Food and Drug Administration.

Revised: 11/2024

PRINCIPAL DISPLAY PANEL - 25 mg Tablet Bottle Label

30 Tablets
NDC59676-278-01

EDURANT®
(rilpivirine) tablets

25 mg

Each tablet contains 27.5 mg of rilpivirine
hydrochloride, which is equivalent to 25 mg
of rilpivirine.

ALERT: Find out about
medicines that should NOT be
taken with EDURANT®from
your healthcare provider.

Rx only

PRINCIPAL DISPLAY PANEL - 2.5 mg Tablet Blister Pack Carton

NDC 59676-280-90
Rx only

EDURANT® PED

(rilpivirine)
tablets for oral suspension

2.5 mg

90 tablets
9 blister cards, 10 tablets each

Attention: EDURANT PED is NOT a substitute for EDURANT

DISPERSE IN DRINKING WATER
Do not crush, chew, or swallow whole, see Instructions for Use